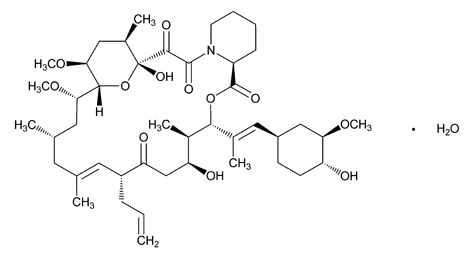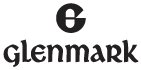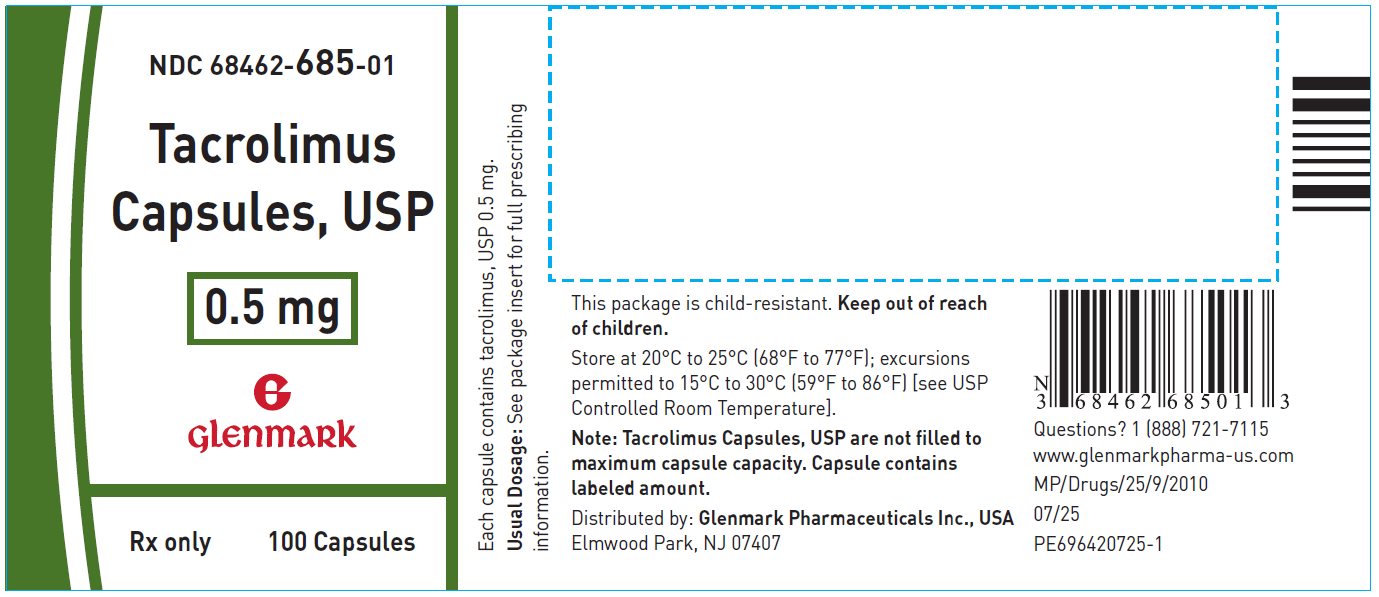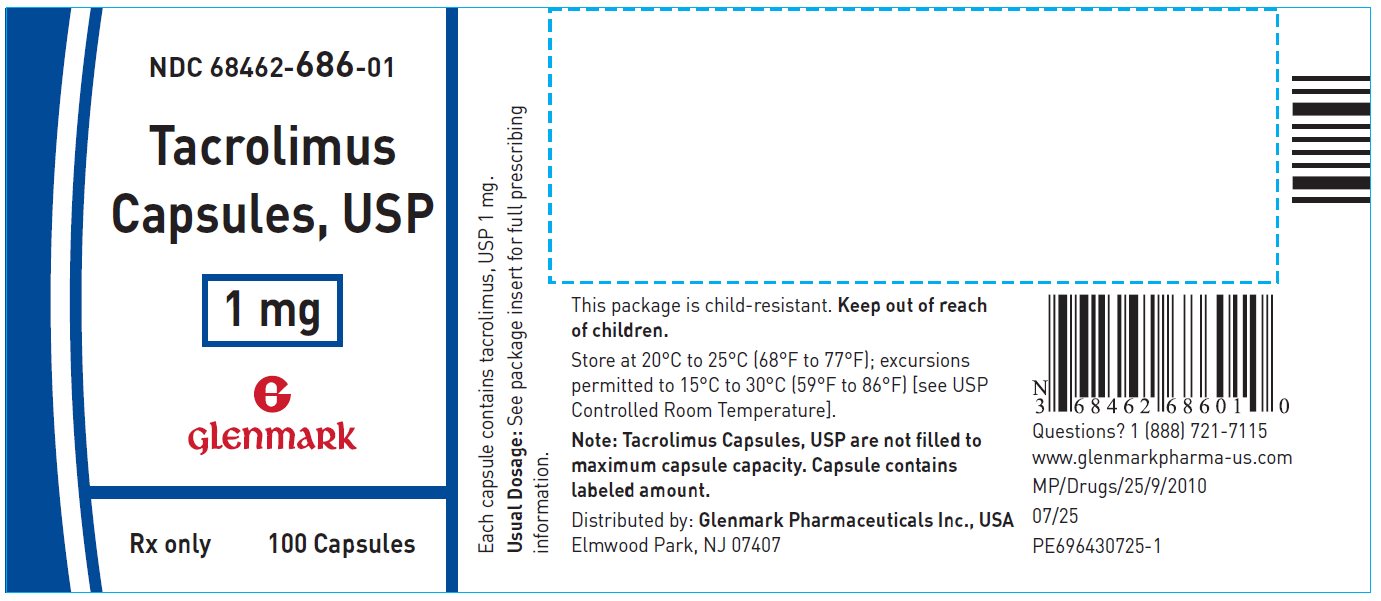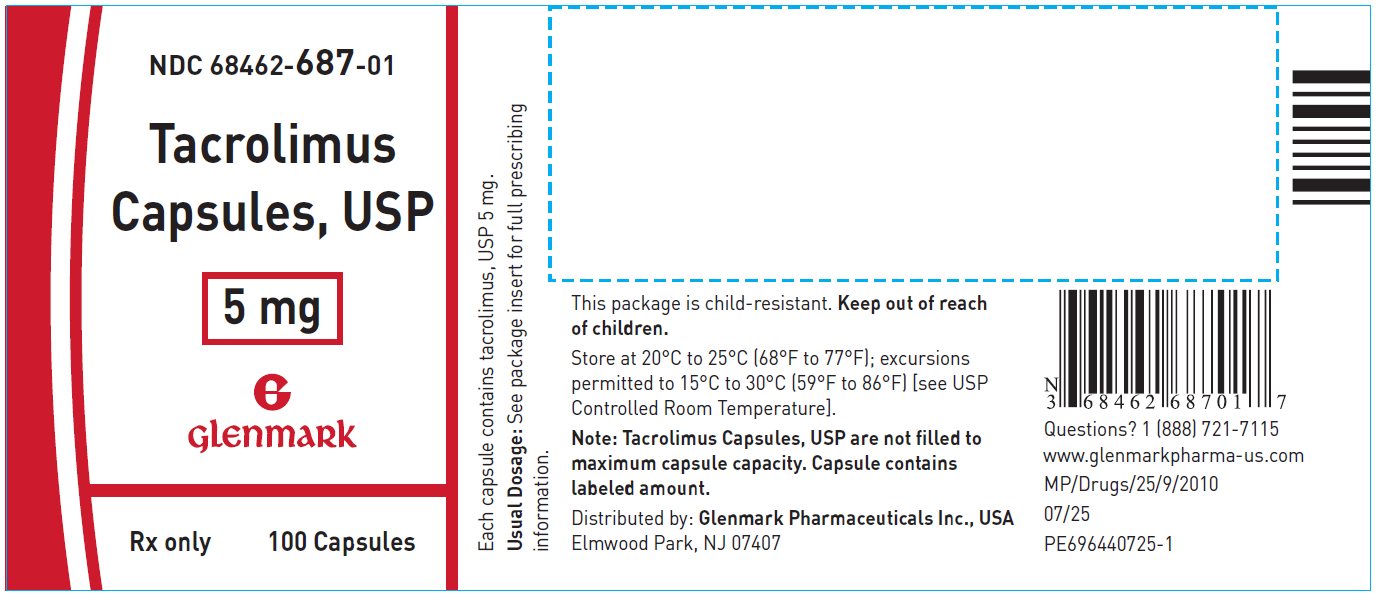 DRUG LABEL: tacrolimus
NDC: 68462-685 | Form: CAPSULE
Manufacturer: Glenmark Pharmaceuticals Inc., USA
Category: prescription | Type: HUMAN PRESCRIPTION DRUG LABEL
Date: 20260121

ACTIVE INGREDIENTS: TACROLIMUS 0.5 mg/1 1
INACTIVE INGREDIENTS: HYPROMELLOSE, UNSPECIFIED; CROSCARMELLOSE SODIUM; LACTOSE MONOHYDRATE; MAGNESIUM STEARATE; GELATIN, UNSPECIFIED; FD&C BLUE NO. 1; FD&C RED NO. 40; D&C YELLOW NO. 10; TITANIUM DIOXIDE; SHELLAC; SODIUM HYDROXIDE; POVIDONE, UNSPECIFIED

HIGHLIGHTS OF PRESCRIBING INFORMATION

These highlights do not include all the information needed to use TACROLIMUS CAPSULES safely and effectively. See full prescribing information for TACROLIMUS CAPSULES.
TACROLIMUS capsules, for oral use
Initial U.S. Approval: 1994

WARNING: MALIGNANCIES AND SERIOUS INFECTIONS

See full prescribing information for complete boxed warning.

Increased risk for developing serious infections and malignancies with tacrolimus or other immunosuppressants that may lead to hospitalization or death. (5.1, 5.2)

1 INDICATIONS AND USAGE

Tacrolimus capsules are a calcineurin-inhibitor immunosuppressant indicated for the prophylaxis of organ rejection in adult and pediatric patients receiving allogeneic liver, kidney or heart transplants in combination with other immunosuppressants. (1.1)

2 DOSAGE AND ADMINISTRATION

- Intravenous (IV) use recommended for patients who cannot tolerate oral formulations (capsules). (2.1, 2.2)
- Administer capsules consistently with or without food. (2.1)
- Therapeutic drug monitoring is recommended. (2.1, 2.6)
- Avoid eating grapefruit or drinking grapefruit juice. (2.1)
- See dosage adjustments for African-American patients (2.2), hepatic and renal impaired. (2.4, 2.5)
- For complete dosing information, see Full Prescribing Information.

ADULT
Patient Population | Initial Oral Dosage | Whole Blood Trough Concentration Range
Kidney Transplant
With azathioprine | 0.2 mg/kg/day capsules, divided in two doses, every 12 hours | Month 1 to 3: 7 to 20 ng/mL; Month 4 to 12: 5 to 15 ng/mL
With MMF/IL-2 receptor antagonist | 0.1 mg/kg/day capsules, divided in two doses, every 12 hours | Month 1 to 12: 4 to 11 ng/mL
Liver Transplant
With corticosteroids only | 0.1 to 0.15 mg/kg/day capsules, divided in two doses, every 12 hours | Month 1 to 12: 5 to 20 ng/mL
Heart Transplant
With azathioprine or MMF | 0.075 mg/kg/day capsules, divided in two doses, every 12 hours | Month 1 to 3: 10 to 20 ng/mL; Month ≥ 4: 5 to 15 ng/mL
PEDIATRIC
Patient Population | Initial Oral Dosage | Whole Blood Trough Concentration Range
Kidney Transplant
 | 0.3 mg/kg/day capsules or oral; suspension, divided in two; doses, every 12 hours | Month 1-12: 5-20 ng/mL
Liver Transplant
 | 0.15 to 0.2 mg/kg/day capsules divided in two doses, every 12 hours | Month 1 to 12: 5 to 20 ng/mL
Heart Transplant
 | 0.3 mg/kg/day* capsules or; oral suspension, divided in two; doses, every 12 hours | Month 1-12: 5-20 ng/mL

MMF= Mycophenolate mofetil

* Dose at 0.1 mg/kg/day if antibody induction treatment is administered.

3 DOSAGE FORMS AND STRENGTHS

- Capsules: 0.5 mg, 1 mg and 5 mg (3)

4 CONTRAINDICATIONS

- Hypersensitivity to tacrolimus or HCO-60 (polyoxyl 60 hydrogenated castor oil). (4)

5 WARNINGS AND PRECAUTIONS

- Not Interchangeable with Extended-Release Tacrolimus Products- Medication Errors: Instruct patients or caregivers to recognize the appearance of tacrolimus capsules. (5.3)
- New Onset Diabetes After Transplant: Monitor blood glucose. (5.4)
- Nephrotoxicity (acute and/or chronic): Reduce the dose; use caution with other nephrotoxic drugs. (5.5)
- Neurotoxicity: Including risk of Posterior Reversible Encephalopathy Syndrome (PRES); monitor for neurologic abnormalities; reduce or discontinue tacrolimus. (5.6)
- Hyperkalemia: Monitor serum potassium levels. Consider carefully before using with other agents also associated with hyperkalemia. (5.7)
- Hypertension: May require antihypertensive therapy. Monitor relevant drug-drug interactions. (5.8)
- Anaphylactic Reactions with IV formulation: Observe patients receiving PROGRAF injection for signs and symptoms of anaphylaxis. (5.9)
- Not recommended for use with sirolimus: Not recommended in liver and heart transplant due to increased risk of serious adverse reactions. (5.10)
- Myocardial Hypertrophy: Consider dose reduction/discontinuation. (5.13)
- Immunizations: Avoid live vaccines. (5.14)
- Pure Red Cell Aplasia: Consider discontinuation of tacrolimus. (5.15)
- Thrombotic Microangiopathy, Including Hemolytic Uremic Syndrome and Thrombotic Thrombocytopenic Purpura: May occur, especially in patients with infections and certain concomitant medications. (5.16)

6 ADVERSE REACTIONS

The most common adverse reactions (≥ 15%) were abnormal renal function, hypertension, diabetes mellitus, fever, CMV infection, tremor, hyperglycemia, leukopenia, infection, anemia, bronchitis, pericardial effusion, urinary tract infection, constipation, diarrhea, headache, abdominal pain, insomnia, paresthesia, peripheral edema, nausea, hyperkalemia, hypomagnesemia, and hyperlipemia. (6.1)

To report SUSPECTED ADVERSE REACTIONS, contact Glenmark Pharmaceuticals Inc., USA at 1 (888) 721-7115 or FDA at 1-800-FDA-1088 or www.fda.gov/medwatch.

7 DRUG INTERACTIONS

- Mycophenolic Acid Products: Can increase MPA exposure after crossover from cyclosporine to tacrolimus; monitor for MPA-related adverse reactions and adjust MMF or MPA dose as needed. (7.1)
- Nelfinavir and Grapefruit Juice: Increased tacrolimus concentrations via CYP3A inhibition; avoid concomitant use. (7.2)
- CYP3A Inhibitors: Increased tacrolimus concentrations; monitor concentrations and adjust tacrolimus dose as needed. (5.11, 7.2)
- CYP3A4 Inducers: Decreased tacrolimus concentrations; monitor concentrations and adjust tacrolimus dose as needed. (5.11,7.2).
- Therapeutic drug monitoring and dose reduction for tacrolimus should be considered when tacrolimus is coadministered with cannabidiol (5.17, 7.3).

8 USE IN SPECIFIC POPULATIONS

Pregnancy: Can cause fetal harm. Advise pregnant women of the potential risk to the fetus. (8.1, 8.3)

FULL PRESCRIBING INFORMATION

WARNING: MALIGNANCIES AND SERIOUS INFECTIONS

Increased risk for developing serious infections and malignancies with tacrolimus or other immunosuppressants that may lead to hospitalization or death. (5.1, 5.2)

1 INDICATIONS AND USAGE

1.1 Prophylaxis of Organ Rejection in Kidney, Liver, or Heart Transplant

Tacrolimus capsules are indicated for the prophylaxis of organ rejection, in adult and pediatric patients receiving allogeneic kidney transplant [see Clinical Studies (14.1)], liver transplant [see Clinical Studies (14.2)] and heart transplant [see Clinical Studies (14.3)] in combination with other immunosuppressants.

2 DOSAGE AND ADMINISTRATION

2.1 Important Administration Instructions

Tacrolimus capsules should not be used without supervision by a physician with experience in immunosuppressive therapy.

Tacrolimus capsules are not interchangeable or substitutable for other tacrolimus extended-release products. This is because rate of absorption following the administration of an extended-release tacrolimus product is not equivalent to that of an immediate-release tacrolimus drug product. Under- or overexposure to tacrolimus may result in graft rejection or other serious adverse reactions. Changes between tacrolimus immediate-release and extended-release dosage forms must occur under physician supervision [see Warnings and Precautions (5.3)].

Intravenous Formulation - Administration Precautions due to Risk of Anaphylaxis

Intravenous use is recommended for patients who cannot tolerate oral formulations, and conversion from intravenous to oral tacrolimus is recommended as soon as oral therapy can be tolerated to minimize the risk of anaphylactic reactions that occurred with injectables containing castor oil derivatives [see Warnings and Precautions (5.9)].

Patients receiving tacrolimus injection should be under continuous observation for at least the first 30 minutes following the start of the infusion and at frequent intervals thereafter. If signs or symptoms of anaphylaxis occur, the infusion should be stopped. An aqueous solution of epinephrine should be available at the bedside as well as a source of oxygen.

Oral Formulation (Capsules)

If patients are able to initiate oral therapy, the recommended starting doses should be initiated. Tacrolimus capsules may be taken with or without food. However, since the presence of food affects the bioavailability of tacrolimus capsules, if taken with food, it should be taken consistently the same way each time [see Clinical Pharmacology (12.3)].

General Administration Instructions

Patients should not eat grapefruit or drink grapefruit juice in combination with tacrolimus capsules [see Drug Interactions (7.2)].

Tacrolimus capsules should not be used simultaneously with cyclosporine. Tacrolimus or cyclosporine should be discontinued at least 24 hours before initiating the other. In the presence of elevated tacrolimus or cyclosporine concentrations, dosing with the other drug usually should be further delayed.

Therapeutic drug monitoring (TDM) is recommended for all patients receiving tacrolimus capsules [see Dosage and Administration (2.6)].

2.2 Dosage Recommendations for Adult Kidney, Liver, or Heart Transplant Patients – Capsules and Injection

Capsules

If patients are able to tolerate oral therapy, the recommended oral starting doses should be initiated. The initial dose of tacrolimus capsules should be administered no sooner than 6 hours after transplantation in the liver or heart transplant patients. In kidney transplant patients, the initial dose of tacrolimus capsules may be administered within 24 hours of transplantation, but should be delayed until renal function has recovered.

The initial oral tacrolimus capsules dosage recommendations for adult patients with kidney, liver, or heart transplants and whole blood trough concentration range are shown in Table 1. Perform therapeutic drug monitoring (TDM) to ensure that patients are within the ranges listed in Table 1.

Table 1. Summary of Initial Oral Tacrolimus Capsules Dosage Recommendations and Whole Blood Trough Concentration Range in Adults

Patient Population | Tacrolimus Capsules* Initial Oral Dosage | Whole Blood Trough Concentration Range
Kidney Transplant
With Azathioprine | 0.2 mg/kg/day, divided in two doses, administered every 12 hours | Month 1 to 3: 7 to 20 ng/mL; Month 4 to 12: 5 to 15 ng/mL
With MMF/IL-2 receptor antagonist† | 0.1 mg/kg/day, divided in two doses, administered every 12 hours | Month 1 to 12: 4 to 11 ng/mL
Liver Transplant
With corticosteroids only | 0.10 to 0.15 mg/kg/day, divided in two doses, administered every 12 hours | Month 1 to 12: 5 to 20 ng/mL
Heart Transplant
With azathioprine or MMF | 0.075 mg/kg/day, divided in two doses, administered every 12 hours | Month 1 to 3: 10 to 20 ng/mL; Month ≥ 4: 5 to 15 ng/mL

* African-American patients may require higher doses compared to Caucasians (see Table 2).

† In a second smaller trial, the initial dose of tacrolimus was 0.15 to 0.2 mg/kg/day and observed tacrolimus concentrations were 6 to 16 ng/mL during month 1 to 3 and 5 to 12 ng/mL during month 4 to 12 [see Clinical Studies (14.1)].

Dosage should be titrated based on clinical assessments of rejection and tolerability. Tacrolimus capsules dosages lower than the recommended initial dosage may be sufficient as maintenance therapy. Adjunct therapy with adrenal corticosteroids is recommended early post-transplant.

The data in kidney transplant patients indicate that the African-American patients required a higher dose to attain comparable trough concentrations compared to Caucasian patients (Table 2) [see Use in Specific Populations (8.8) and Clinical Pharmacology (12.3)].

Table 2. Comparative Dose and Trough Concentrations Based on Race
Time After Transplant | Caucasian N = 114 |  | African-American N = 56
Time After Transplant | Dose (mg/kg) | Trough Concentrations (ng/mL) | Dose (mg/kg) | Trough Concentrations (ng/mL)
Day 7 | 0.18 | 12 | 0.23 | 10.9
Month 1 | 0.17 | 12.8 | 0.26 | 12.9
Month 6 | 0.14 | 11.8 | 0.24 | 11.5
Month 12 | 0.13 | 10.1 | 0.19 | 11

Intravenous Injection

PROGRAF injection should be used only as a continuous intravenous infusion and should be discontinued as soon as the patient can tolerate oral administration. The first dose of tacrolimus capsules should be given 8 to 12 hours after discontinuing the intravenous infusion of PROGRAF.

The recommended starting dose of PROGRAF injection is 0.03 to 0.05 mg/kg/day in kidney or liver transplant and 0.01 mg/kg/day in heart transplant given as a continuous intravenous infusion. Adult patients should receive doses at the lower end of the dosing range. Concomitant adrenal corticosteroid therapy is recommended early post-transplantation.

The whole blood trough concentration range described in Table 1 pertains to oral administration of tacrolimus only; while

monitoring tacrolimus concentrations in patients receiving PROGRAF injection as a continuous intravenous infusion may

have some utility, the observed concentrations will not represent comparable exposures to those estimated by the trough

concentrations observed in patients on oral therapy.

Anaphylactic reactions have occurred with injectables containing castor oil derivatives, such as PROGRAF injection. Therefore, monitoring for signs and symptoms of anaphylaxis is recommended [see Warnings and Precautions (5.9)].

2.3 Dosage Recommendations for Pediatric Kidney, Liver or Heart Transplant Patients

Oral formulation (capsules)

Pediatric patients, in general, need higher tacrolimus doses compared to adults: the higher dose requirements may decrease as the child grows older. Recommendations for the initial oral dosage for pediatric transplant patients and whole blood trough concentration range are shown in Table 3. Perform TDM to ensure that patients are within the ranges listed in Table 3.

Table 3. Summary of Initial Tacrolimus Capsules Dosage Recommendations and Whole Blood Trough Concentration Range in Children

Patient Population | Initial Tacrolimus Capsules Dosing | Whole Blood Trough Concentration Range
Pediatric kidney transplant patients | 0.3 mg/kg/day capsules or oral suspension, divided in two doses, administered every 12 hours | Month 1-12: 5-20 ng/mL
Pediatric liver transplant patients*,† | 0.15 to 0.2 mg/kg/day capsules divided in two doses, administered every 12 hours | Month 1 to 12: 5 to 20 ng/mL
Pediatric heart transplant patients | 0.3 mg/kg/day† capsules or oral; suspension, divided in two doses,; administered every 12 hours | Month 1-12: 5-20 ng/mL

* See Clinical Studies (14.2), Liver Transplantation.

† Dose at 0.1 mg/kg/day if antibody induction treatment is administered.

For conversion of pediatric patients from PROGRAF granules to tacrolimus capsules or from tacrolimus capsules to PROGRAF granules, the total daily dose should remain the same. Following conversion from one formulation to another formulation of tacrolimus, therapeutic drug monitoring is recommended [see Dosage and Administration (2.6)].

Intravenous Injection

If a patient is unable to receive an oral formulation, the patient may be started on PROGRAF injection. For pediatric liver transplant patients, the intravenous dose is 0.03 to 0.05 mg/kg/day.

2.4 Dosage Modification for Patients with Renal Impairment

Due to its potential for nephrotoxicity, consider dosing tacrolimus capsules at the lower end of the therapeutic dosing range in patients who have received a liver or heart transplant, and have pre-existing renal impairment. Further reductions in dose below the targeted range may be required.

In kidney transplant patients with post-operative oliguria, the initial dose of tacrolimus capsules should be administered no sooner than 6 hours and within 24 hours of transplantation, but may be delayed until renal function shows evidence of recovery [see Dosage and Administration (2.2), Warnings and Precautions (5.5), Use in Specific Populations (8.6), and Clinical Pharmacology (12.3)].

2.5 Dosage Modification for Patients with Hepatic Impairment

Due to the reduced clearance and prolonged half-life, patients with severe hepatic impairment (Child-Pugh ≥ 10) may require lower doses of tacrolimus capsules. Close monitoring of blood concentrations is warranted.

The use of tacrolimus capsules in liver transplant recipients experiencing post-transplant hepatic impairment may be associated with increased risk of developing renal insufficiency related to high whole blood concentrations of tacrolimus. These patients should be monitored closely, and dosage adjustments should be considered. Some evidence suggests that lower doses should be used in these patients [see Dosage and Administration (2.2), Warnings and Precautions (5.5), Use in Specific Populations (8.7), and Clinical Pharmacology (12.3)].

2.6 Therapeutic Drug Monitoring

Monitoring of tacrolimus blood concentrations in conjunction with other laboratory and clinical parameters is considered an essential aid to patient management for the evaluation of rejection, toxicity, dose adjustments, and compliance. Whole blood trough concentration range can be found in Table 1.

Factors influencing frequency of monitoring include but are not limited to hepatic or renal dysfunction, the addition or discontinuation of potentially interacting drugs and the post-transplant time. Blood concentration monitoring is not a replacement for renal and liver function monitoring and tissue biopsies. Data from clinical trials show that tacrolimus whole blood concentrations were most variable during the first week post-transplantation.

The relative risks of toxicity and efficacy failure are related to tacrolimus whole blood trough concentrations. Therefore, monitoring of whole blood trough concentrations is recommended to assist in the clinical evaluation of toxicity and efficacy failure.

Methods commonly used for the assay of tacrolimus include high-performance liquid chromatography with tandem mass spectrometric detection (HPLC/MS/MS) and immunoassays. Immunoassays may react with metabolites as well as the parent compound. Therefore, assay results obtained with immunoassays may have a positive bias relative to results of HPLC/MS. The bias may depend upon the specific assay and laboratory. Comparison of the concentrations in published literature to patient concentrations using the current assays must be made with detailed knowledge of the assay methods and biological matrices employed. Whole blood is the matrix of choice and specimens should be collected into tubes containing ethylene diamine tetraacetic acid (EDTA) anticoagulant. Heparin anticoagulation is not recommended because of the tendency to form clots on storage. Samples which are not analyzed immediately should be stored at room temperature or in a refrigerator and assayed within 7 days; see assay instructions for specifics. If samples are to be kept longer, they should be deep frozen at -20°C. One study showed drug recovery > 90% for samples stored at -20°C for 6 months, with reduced recovery observed after 6 months.

3 DOSAGE FORMS AND STRENGTHS

Tacrolimus Capsules, USP are hard gelatin capsules for oral administration containing anhydrous tacrolimus, USP as follows:

- 0.5 mg: Size “4” hard gelatin capsule with light yellow cap and light yellow body, imprinted with a Glenmark logo “G” on the cap and “685” on the body in red ink, filled with white to off-white granular powder.
- 1 mg: Size “4” hard gelatin capsule with white cap and white body, imprinted with a Glenmark logo “G” on the cap and “686” on the body in red ink, filled with white to off-white granular powder.
- 5 mg: Size “4” hard gelatin capsule with greyish red cap and greyish red body, imprinted with a Glenmark logo “G” on the cap and “687” on the body in white ink, filled with white to off-white granular powder.

4 CONTRAINDICATIONS

Tacrolimus capsules are contraindicated in patients with a hypersensitivity to tacrolimus. Tacrolimus injection is contraindicated in patients with a hypersensitivity to HCO-60 (polyoxyl 60 hydrogenated castor oil). Hypersensitivity symptoms reported include dyspnea, rash, pruritus, and acute respiratory distress syndrome [see Adverse Reactions (6)].

5 WARNINGS AND PRECAUTIONS

5.1 Lymphoma and Other Malignancies

Patients receiving immunosuppressants, including tacrolimus, are at increased risk of developing lymphomas and other malignancies, particularly of the skin. The risk appears to be related to the intensity and duration of immunosuppression rather than to the use of any specific agent.

As usual for patients with increased risk for skin cancer, examine patients for skin changes; exposure to sunlight and UV light should be limited by wearing protective clothing and using a broad-spectrum sunscreen with a high protection factor.

Post-transplant lymphoproliferative disorder (PTLD) has been reported in immunosuppressed organ transplant recipients. The majority of PTLD events appear related to Epstein-Barr Virus (EBV) infection. The risk of PTLD appears greatest in those individuals who are EBV seronegative, a population which includes many young children. Monitor EBV serology during treatment.

5.2 Serious Infections

Patients receiving immunosuppressants, including tacrolimus, are at increased risk of developing bacterial, viral, fungal, and protozoal infections, including opportunistic infections. These infections may lead to serious, including fatal, outcomes. Serious viral infections reported include:

- Polyomavirus-associated nephropathy (PVAN), mostly due to BK virus infection
- JC virus-associated progressive multifocal leukoencephalopathy (PML)
- Cytomegalovirus infections: CMV seronegative transplant patients who receive an organ from a CMV seropositive donor disease are at higher risk of developing CMV viremia and CMV disease.

Monitor for the development of infection and adjust the immunosuppressive regimen to balance the risk of rejection with the risk of infection [see Adverse Reactions (6.1, 6.2)].

5.3 Not Interchangeable with Extended-Release Tacrolimus Products - Medication Errors

Medication errors, including substitution and dispensing errors, between tacrolimus immediate-release products and tacrolimus extended-release products were reported outside the U.S. This led to serious adverse reactions, including graft rejection, or other adverse reactions due to under-or overexposure to tacrolimus. Tacrolimus capsules are not interchangeable or substitutable for tacrolimus extended-release products. Changes between tacrolimus immediate-release and extended-release dosage forms must occur under physician supervision. Instruct patients and caregivers to recognize the appearance of tacrolimus capsules dosage forms [see Dosage Forms and Strengths (3)] and to confirm with the healthcare provider if a different product is dispensed.

5.4 New Onset Diabetes After Transplant

Tacrolimus was shown to cause new onset diabetes mellitus in clinical trials of kidney, liver, or heart transplantation. New onset diabetes after transplantation may be reversible in some patients. African-American and Hispanic kidney transplant patients are at an increased risk. Blood glucose concentrations should be monitored closely in patients using tacrolimus [see Adverse Reactions (6.1)].

5.5 Nephrotoxicity due to Tacrolimus and Drug Interactions

Tacrolimus, like other calcineurin inhibitors, can cause acute or chronic nephrotoxicity in transplant patients due to its vasoconstrictive effect on renal vasculature, toxic tubulopathy and tubular-interstitial effects. Nephrotoxicity was reported in clinical trials [see Adverse Reactions (6.1)].

Acute renal impairment associated with tacrolimus toxicity can result in high serum creatinine, hyperkalemia, decreased secretion of urea and hyperuricemia, and is usually reversible. In patients with elevated serum creatinine and tacrolimus whole blood trough concentrations greater than the recommended range, consider dosage reduction or temporary interruption of tacrolimus administration.

The risk for nephrotoxicity may increase when tacrolimus is concomitantly administered with CYP3A inhibitors (by increasing tacrolimus whole blood concentrations) or drugs associated with nephrotoxicity (e.g., aminoglycosides, ganciclovir, amphotericin B, cisplatin, nucleotide reverse transcriptase inhibitors, protease inhibitors). When tacrolimus is used concurrently with other known nephrotoxic drugs, monitor renal function and tacrolimus blood concentrations, and adjust doses of both tacrolimus and/or concomitant medications during concurrent use [see Drug Interactions (7.2)].

5.6 Neurotoxicity

Tacrolimus may cause a spectrum of neurotoxicities. The most severe neurotoxicities include posterior reversible encephalopathy syndrome (PRES), delirium, seizure and coma; others include tremors, paresthesias, headache, mental status changes, and changes in motor and sensory functions [see Adverse Reactions (6.1, 6.2)]. As symptoms may be associated with tacrolimus whole blood trough concentrations at or above the recommended range, monitor for neurologic symptoms and consider dosage reduction or discontinuation of tacrolimus if neurotoxicity occurs.

5.7 Hyperkalemia

Hyperkalemia has been reported with tacrolimus use. Serum potassium levels should be monitored. Careful consideration should be given prior to use of other agents also associated with hyperkalemia (e.g., potassium-sparing diuretics, ACE inhibitors, angiotensin receptor blockers) during tacrolimus therapy [see Adverse Reactions (6.1)]. Monitor serum potassium levels periodically during treatment.

5.8 Hypertension

Hypertension is a common adverse effect of tacrolimus therapy and may require antihypertensive therapy [see Adverse Reactions (6.1)]. The control of blood pressure can be accomplished with any of the common antihypertensive agents, though careful consideration should be given prior to use of antihypertensive agents associated with hyperkalemia (e.g., potassium-sparing diuretics, ACE inhibitors, angiotensin receptor blockers) [see Warnings and Precautions (5.7)]. Calcium-channel blocking agents may increase tacrolimus blood concentrations and therefore require dosage reduction of tacrolimus [see Drug Interactions (7.2)].

5.9 Anaphylactic Reactions with PROGRAF Injection

Anaphylactic reactions have occurred with injectables containing castor oil derivatives, including tacrolimus, in a small percentage of patients (0.6%). The exact cause of these reactions is not known. Tacrolimus injection should be reserved for patients who are unable to take tacrolimus orally. Monitor patients for anaphylaxis when using the intravenous route of administration [see Dosage and Administration (2.1)].

5.10 Not Recommended for Use with Sirolimus

Tacrolimus is not recommended for use with sirolimus:

- The use of sirolimus with tacrolimus in studies of de novo liver transplant patients was associated with an excess mortality, graft loss, and hepatic artery thrombosis (HAT), and is not recommended.
- The use of sirolimus (2 mg per day) with tacrolimus in heart transplant patients in a U.S. trial was associated with increased risk of renal function impairment, wound healing complications, and insulin-dependent post-transplant diabetes mellitus, and is not recommended [see Clinical Studies (14.3)].
- The use of sirolimus with tacrolimus may increase the risk of thrombotic microangiopathy [see Warnings and Precautions (5.16)].

5.11 Interactions with CYP3A4 Inhibitors and Inducers

When co-administering tacrolimus with strong CYP3A4 inhibitors (e.g., telaprevir, boceprevir, ritonavir, ketoconazole, itraconazole, voriconazole, clarithromycin) and strong inducers (e.g., rifampin, rifabutin), adjustments in the dosing regimen of tacrolimus and subsequent frequent monitoring of tacrolimus whole blood trough concentrations and tacrolimus-associated adverse reactions are recommended. A rapid, sharp rise in tacrolimus levels has been reported after co-administration with a strong CYP3A4 inhibitor, clarithromycin, despite an initial reduction of tacrolimus dose. Early and frequent monitoring of tacrolimus whole blood trough levels is recommended [see Drug Interactions (7.2)].

5.12 QT Prolongation

Tacrolimus may prolong the QT/QTc interval and may cause Torsades de pointes. Avoid tacrolimus in patients with congenital long QT syndrome. In patients with congestive heart failure, bradyarrhythmias, those taking certain antiarrhythmic medications or other medicinal products that lead to QT prolongation, and those with electrolyte disturbances such as hypokalemia, hypocalcemia, or hypomagnesemia, consider obtaining electrocardiograms and monitoring electrolytes (magnesium, potassium, calcium) periodically during treatment.

When co-administering tacrolimus with other substrates and/or inhibitors of CYP3A4 that also have the potential to prolong the QT interval, a reduction in tacrolimus dose, frequent monitoring of tacrolimus whole blood concentrations, and monitoring for QT prolongation is recommended. Use of tacrolimus with amiodarone has been reported to result in increased tacrolimus whole blood concentrations with or without concurrent QT prolongation [see Drug Interactions (7.2)].

5.13 Myocardial Hypertrophy

Myocardial hypertrophy has been reported in infants, children, and adults, particularly those with high tacrolimus trough concentrations, and is generally manifested by echocardiographically demonstrated concentric increases in left ventricular posterior wall and interventricular septum thickness. This condition appears reversible in most cases following dose reduction or discontinuance of therapy. In patients who develop renal failure or clinical manifestations of ventricular dysfunction while receiving tacrolimus therapy, echocardiographic evaluation should be considered. If myocardial hypertrophy is diagnosed, dosage reduction or discontinuation of tacrolimus should be considered [see Adverse Reactions (6.2)].

5.14 Immunizations

Whenever possible, administer the complete complement of vaccines before transplantation and treatment with tacrolimus.

The use of live vaccines should be avoided during treatment with tacrolimus; examples include (not limited to) the following: intranasal influenza, measles, mumps, rubella, oral polio, BCG, yellow fever, varicella, and TY21a typhoid vaccines.

Inactivated vaccines noted to be safe for administration after transplantation may not be sufficiently immunogenic during treatment with tacrolimus.

5.15 Pure Red Cell Aplasia

Cases of pure red cell aplasia (PRCA) have been reported in patients treated with tacrolimus. A mechanism for tacrolimus-induced PRCA has not been elucidated. All patients reported risk factors for PRCA such as parvovirus B19 infection, underlying disease, or concomitant medications associated with PRCA. If PRCA is diagnosed, discontinuation of tacrolimus should be considered [see Adverse Reactions (6.2)].

5.16 Thrombotic Microangiopathy (Including Hemolytic Uremic Syndrome and Thrombotic Thrombocytopenic Purpura)

Cases of thrombotic microangiopathy (TMA), including hemolytic uremic syndrome (HUS) and thrombotic thrombocytopenic purpura (TTP), have been reported in patients treated with tacrolimus. TMA may have a multifactorial etiology. Risk factors for TMA that can occur in transplant patients include, for example, severe infections, graft-versus- host disease (GVHD), Human Leukocyte Antigen (HLA) mismatch, the use of calcineurin inhibitors and mammalian target of rapamycin (mTOR) inhibitors. These risk factors may, either alone or combined, contribute to the risk of TMA.

In patients with signs and symptoms of TMA, consider tacrolimus as a risk factor. Concurrent use of tacrolimus and mTOR inhibitors may contribute to the risk of TMA.

5.17 Cannabidiol Drug Interactions

When cannabidiol and tacrolimus are coadministered, closely monitor for an increase in tacrolimus blood levels and for adverse reactions suggestive of tacrolimus toxicity. A dose reduction of tacrolimus should be considered as needed when tacrolimus is coadministered with cannabidiol [see Dosage and Administration (2.2,2.6) and Drug Interactions (7.3)].

6 ADVERSE REACTIONS

The following serious and otherwise important adverse drug reactions are discussed in greater detail in other sections of labeling:

- Lymphoma and Other Malignancies [see Warnings and Precautions (5.1)]
- Serious Infections [see Warnings and Precautions (5.2)]
- New Onset Diabetes After Transplant [see Warnings and Precautions (5.4)]
- Nephrotoxicity [see Warnings and Precautions (5.5)]
- Neurotoxicity [see Warnings and Precautions (5.6)]
- Hyperkalemia [see Warnings and Precautions (5.7)]
- Hypertension [see Warnings and Precautions (5.8)]
- Anaphylactic Reactions with PROGRAF Injection [see Warnings and Precautions (5.9)]
- Myocardial Hypertrophy [see Warnings and Precautions (5.13)]
- Pure Red Cell Aplasia [see Warnings and Precautions (5.15)]
- Thrombotic Microangiopathy, Including Hemolytic Uremic Syndrome and Thrombotic Thrombocytopenic Purpura [see Warnings and Precautions (5.16)]

6.1 Clinical Studies Experience

Because clinical trials are conducted under widely varying conditions, adverse reaction rates observed in the clinical trials of a drug cannot be directly compared to rates in the clinical trials of another drug and may not reflect the rates observed in practice. In addition, the clinical trials were not designed to establish comparative differences across study arms with regards to the adverse reactions discussed below.

Kidney Transplantation

The incidence of adverse reactions was determined in three randomized kidney transplant trials. One of the trials used azathioprine (AZA) and corticosteroids and two of the trials used mycophenolate mofetil (MMF) and corticosteroids concomitantly for maintenance immunosuppression.

Tacrolimus-based immunosuppression in conjunction with azathioprine and corticosteroids following kidney transplantation was assessed in a trial where 205 patients received tacrolimus-based immunosuppression and 207 patients received cyclosporine-based immunosuppression. The trial population had a mean age of 43 years (mean ± SD was 43 ± 13 years on tacrolimus and 44 ± 12 years on cyclosporine arm), the distribution was 61% male, and the composition was White (58%), African-American (25%), Hispanic (12%), and Other (5%). The 12-month post-transplant information from this trial is presented below.

The most common adverse reactions (≥ 30%) observed in tacrolimus-treated kidney transplant patients are: infection, tremor, hypertension, abnormal renal function, constipation, diarrhea, headache, abdominal pain, insomnia, nausea, hypomagnesemia, urinary tract infection, hypophosphatemia, peripheral edema, asthenia, pain, hyperlipidemia, hyperkalemia, and anemia. Based on reported adverse reaction terms related to decreased renal function, nephrotoxicity was reported in approximately 52% of kidney transplantation patients.

Adverse reactions that occurred in ≥ 15% of kidney transplant patients treated with tacrolimus in conjunction with azathioprine are presented below:

Table 4. Kidney Transplantation: Adverse Reactions Occurring in ≥ 15% of Patients Treated with Tacrolimus in Conjunction with Azathioprine (AZA)
 | Tacrolimus/AZA (N = 205) | Cyclosporine/AZA (N = 207)
Nervous System
Tremor | 54% | 34%
Headache | 44% | 38%
Insomnia | 32% | 30%
Paresthesia | 23% | 16%
Dizziness | 19% | 16%
Gastrointestinal
Diarrhea | 44% | 41%
Nausea | 38% | 36%
Constipation | 35% | 43%
Vomiting | 29% | 23%
Dyspepsia | 28% | 20%
Cardiovascular
Hypertension | 50% | 52%
Chest Pain | 19% | 13%
Urogenital
Creatinine Increased | 45% | 42%
Urinary Tract Infection | 34% | 35%
Metabolic and Nutritional
Hypophosphatemia | 49% | 53%
Hypomagnesemia | 34% | 17%
Hyperlipemia | 31% | 38%
Hyperkalemia | 31% | 32%
Diabetes Mellitus | 24% | 9%
Hypokalemia | 22% | 25%
Hyperglycemia | 22% | 16%
Edema | 18% | 19%
Hemic and Lymphatic
Anemia | 30% | 24%
Leukopenia | 15% | 17%
Miscellaneous
Infection | 45% | 49%
Peripheral Edema | 36% | 48%
Asthenia | 34% | 30%
Abdominal Pain | 33% | 31%
Pain | 32% | 30%
Fever | 29% | 29%
Back Pain | 24% | 20%
Respiratory System
Dyspnea | 22% | 18%
Cough Increased | 18% | 15%
Musculoskeletal
Arthralgia | 25% | 24%
Skin
Rash | 17% | 12%
Pruritus | 15% | 7%

Two trials were conducted for tacrolimus-based immunosuppression in conjunction with MMF and corticosteroids. In the non-US trial (Study 1), the incidence of adverse reactions was based on 1195 kidney transplant patients that received tacrolimus (Group C, n = 403), or one of two cyclosporine (CsA) regimens (Group A, n = 384 and Group B, n = 408) in combination with MMF and corticosteroids; all patients, except those in one of the two cyclosporine groups, also received induction with daclizumab. The trial population had a mean age of 46 years (range 17 to 76); the distribution was 65% male, and the composition was 93% Caucasian. The 12-month post-transplant information from this trial is presented below.

Adverse reactions that occurred in ≥ 10% of kidney transplant patients treated with tacrolimus in conjunction with MMF in Study 1 [Note: This trial was conducted entirely outside of the United States. Such trials often report a lower incidence of adverse reactions in comparison to U.S. trials] are presented below:

Table 5. Kidney Transplantation: Adverse Reactions Occurring in ≥ 10% of Patients Treated with Tacrolimus in Conjunction with MMF (Study 1)
 | Tacrolimus (Group C); (N = 403) | Cyclosporine (Group A); (N = 384) | Cyclosporine (Group B); (N = 408)
Diarrhea | 25% | 16% | 13%
Urinary Tract Infection | 24% | 28% | 24%
Anemia | 17% | 19% | 17%
Hypertension | 13% | 14% | 12%
Leukopenia | 13% | 10% | 10%
Edema Peripheral | 11% | 12% | 13%
Hyperlipidemia | 10% | 15% | 13%
Key: Group A = CsA/MMF/CS, B = CsA/MMF/CS/Daclizumab, C = Tac/MMF/CS/Daclizumab
CsA = Cyclosporine, CS = Corticosteroids, Tac = Tacrolimus, MMF = mycophenolate mofetil

In the U.S. trial (Study 2) with tacrolimus-based immunosuppression in conjunction with MMF and corticosteroids, 424 kidney transplant patients received tacrolimus (n = 212) or cyclosporine (n = 212) in combination with MMF 1 gram twice daily, basiliximab induction, and corticosteroids. The trial population had a mean age of 48 years (range 17 to 77); the distribution was 63% male, and the composition was White (74%), African-American (20%), Asian (3%), and Other (3%). The 12-month post-transplant information from this trial is presented below.

Adverse reactions that occurred in ≥ 15% of kidney transplant patients treated with tacrolimus in conjunction with MMF in Study 2 are presented below:

Table 6. Kidney Transplantation: Adverse Reactions Occurring in ≥ 15% of Patients Treated with Tacrolimus in Conjunction with MMF (Study 2)
 | Tacrolimus/MMF (N = 212) | Cyclosporine/MMF (N = 212)
Gastrointestinal Disorders
Diarrhea | 44% | 26%
Nausea | 39% | 47%
Constipation | 36% | 41%
Vomiting | 26% | 25%
Dyspepsia | 18% | 15%
Injury, Poisoning, and Procedural Complications
Post-Procedural Pain | 29% | 27%
Incision Site Complication | 28% | 23%
Graft Dysfunction | 24% | 18%
Metabolism and Nutrition Disorders
Hypomagnesemia | 28% | 22%
Hypophosphatemia | 28% | 21%
Hyperkalemia | 26% | 19%
Hyperglycemia | 21% | 15%
Hyperlipidemia | 18% | 25%
Hypokalemia | 16% | 18%
Nervous System Disorders
Tremor | 34% | 20%
Headache | 24% | 25%
Blood and Lymphatic System Disorders
Anemia | 30% | 28%
Leukopenia | 16% | 12%
Miscellaneous
Edema Peripheral | 35% | 46%
Hypertension | 32% | 35%
Insomnia | 30% | 21%
Urinary Tract Infection | 26% | 22%
Blood Creatinine Increased | 23% | 23%

Less frequently observed adverse reactions in kidney transplantation patients are described under the subsection “Less Frequently Reported Adverse Reactions (> 3% and < 15%) in Liver, Kidney, and Heart Transplant Studies.”

Liver Transplantation

There were two randomized comparative liver transplant trials. In the U.S. trial, 263 adult and pediatric patients received tacrolimus and steroids and 266 patients received cyclosporine-based immunosuppressive regimen (CsA/AZA). The trial population had a mean age of 44 years (range 0.4 to 70); the distribution was 52% male, and the composition was White (78%), African-American (5%), Asian (2%), Hispanic (13%), and Other (2%). In the European trial, 270 patients received tacrolimus and steroids and 275 patients received CsA/AZA. The trial population had a mean age of 46 years (range 15 to 68); the distribution was 59% male, and the composition was White (95.4%), Black (1%), Asian (2%), and Other (2%).

The proportion of patients reporting more than one adverse event was > 99% in both the tacrolimus group and the CsA/AZA group. Precautions must be taken when comparing the incidence of adverse reactions in the U.S. trial to that in the European trial. The 12-month post-transplant information from the U.S. trial and from the European trial is presented below. The two trials also included different patient populations and patients were treated with immunosuppressive regimens of differing intensities. Adverse reactions reported in ≥ 15% in tacrolimus patients (combined trial results) are presented below for the two controlled trials in liver transplantation.

The most common adverse reactions (≥ 40%) observed in tacrolimus-treated liver transplant patients are: tremor, headache, diarrhea, hypertension, nausea, abnormal renal function, abdominal pain, insomnia, paresthesia, anemia, pain, fever, asthenia, hyperkalemia, hypomagnesemia, and hyperglycemia. These all occur with oral and IV administration of tacrolimus and some may respond to a reduction in dosing (e.g., tremor, headache, paresthesia, hypertension). Diarrhea was sometimes associated with other gastrointestinal complaints such as nausea and vomiting. Based on reported adverse reaction terms related to decreased renal function, nephrotoxicity was reported in approximately 40% and 36% of liver transplantation patients receiving tacrolimus in the U.S. and European randomized trials.

Table 7. Liver Transplantation: Adverse Reactions Occurring in ≥ 15% of Patients Treated with Tacrolimus
 | U.S. TRIAL |  | EUROPEAN TRIAL
 | Tacrolimus (N = 250) | Cyclosporine/AZA (N = 250) | Tacrolimus (N = 264) | Cyclosporine/AZA (N = 265)
Nervous System
Headache | 64% | 60% | 37% | 26%
Insomnia | 64% | 68% | 32% | 23%
Tremor | 56% | 46% | 48% | 32%
Paresthesia | 40% | 30% | 17% | 17%
Gastrointestinal
Diarrhea | 72% | 47% | 37% | 27%
Nausea | 46% | 37% | 32% | 27%
LFT Abnormal | 36% | 30% | 6% | 5%
Anorexia | 34% | 24% | 7% | 5%
Vomiting | 27% | 15% | 14% | 11%
Constipation | 24% | 27% | 23% | 21%
Cardiovascular
Hypertension | 47% | 56% | 38% | 43%
Urogenital
Kidney Function Abnormal | 40% | 27% | 36% | 23%
Creatinine Increased | 39% | 25% | 24% | 19%
BUN Increased | 30% | 22% | 12% | 9%
Oliguria | 18% | 15% | 19% | 12%
Urinary Tract Infection | 16% | 18% | 21% | 19%
Metabolic and Nutritional
Hypomagnesemia | 48% | 45% | 16% | 9%
Hyperglycemia | 47% | 38% | 33% | 22%
Hyperkalemia | 45% | 26% | 13% | 9%
Hypokalemia | 29% | 34% | 13% | 16%
Hemic and Lymphatic
Anemia | 47% | 38% | 5% | 1%
Leukocytosis | 32% | 26% | 8% | 8%
Thrombocytopenia | 24% | 20% | 14% | 19%
Miscellaneous
Pain | 63% | 57% | 24% | 22%
Abdominal Pain | 59% | 54% | 29% | 22%
Asthenia | 52% | 48% | 11% | 7%
Fever | 48% | 56% | 19% | 22%
Back Pain | 30% | 29% | 17% | 17%
Ascites | 27% | 22% | 7% | 8%
Peripheral Edema | 26% | 26% | 12% | 14%
Respiratory System
Pleural Effusion | 30% | 32% | 36% | 35%
Dyspnea | 29% | 23% | 5% | 4%
Atelectasis | 28% | 30% | 5% | 4%
Skin and Appendages
Pruritus | 36% | 20% | 15% | 7%
Rash | 24% | 19% | 10% | 4%

Less frequently observed adverse reactions in liver transplantation patients are described under the subsection “Less Frequently Reported Adverse Reactions (> 3% and < 15%) in Liver, Kidney, and Heart Transplant Studies.”

Heart Transplantation

The incidence of adverse reactions was determined based on two trials in primary orthotopic heart transplantation. In a trial conducted in Europe, 314 patients received a regimen of antibody induction, corticosteroids, and azathioprine (AZA) in combination with tacrolimus (n = 157) or cyclosporine (n = 157) for 18 months. The trial population had a mean age of 51 years (range 18 to 65); the distribution was 82% male, and the composition was White (96%), Black (3%), and Other (1%).

The most common adverse reactions (≥ 15%) observed in tacrolimus-treated heart transplant patients are: abnormal renal function, hypertension, diabetes mellitus, CMV infection, tremor, hyperglycemia, leukopenia, infection, anemia, bronchitis, pericardial effusion, urinary tract infection, and hyperlipemia. Based on reported adverse reaction terms related to decreased renal function, nephrotoxicity was reported in approximately 59% of heart transplantation patients in the European trial.

Adverse reactions in heart transplant patients in the European trial are presented below:

Table 9. Heart Transplantation: Adverse Reactions Occurring in ≥ 15% of Patients Treated with Tacrolimus in Conjunction with Azathioprine (AZA)
 | Tacrolimus/AZA (N = 157) | Cyclosporine/AZA (N = 157)
Cardiovascular System
Hypertension | 62% | 69%
Pericardial Effusion | 15% | 14%
Body as a Whole
CMV Infection | 32% | 30%
Infection | 24% | 21%
Metabolic and Nutritional Disorders
Diabetes Mellitus | 26% | 16%
Hyperglycemia | 23% | 17%
Hyperlipemia | 18% | 27%
Hemic and Lymphatic System
Anemia | 50% | 36%
Leukopenia | 48% | 39%
Urogenital System
Kidney Function Abnormal | 56% | 57%
Urinary Tract Infection | 16% | 12%
Respiratory System
Bronchitis | 17% | 18%
Nervous System
Tremor | 15% | 6%

In the European trial, the cyclosporine trough concentrations were above the pre-defined target range (i.e., 100 ng/mL to 200 ng/mL) at Day 122 and beyond in 32% to 68% of the patients in the cyclosporine treatment arm, whereas the tacrolimus trough concentrations were within the pre-defined target range (i.e., 5 ng/mL to 15 ng/mL) in 74% to 86% of the patients in the tacrolimus treatment arm.

In a U.S. trial, the incidence of adverse reactions was based on 331 heart transplant patients that received corticosteroids and tacrolimus in combination with sirolimus (n=109), tacrolimus in combination with MMF (n=107) or cyclosporine modified in combination with MMF (n=115) for 1 year. The trial population had a mean age of 53 years (range 18 to 75); the distribution was 78% male, and the composition was White (83%), African-American (13%) and Other (4%).

Only selected targeted treatment-emergent adverse reactions were collected in the U.S. heart transplantation trial. Those reactions that were reported at a rate of 15% or greater in patients treated with tacrolimus and MMF include the following: any target adverse reactions (99%), hypertension (89%), hyperglycemia requiring antihyperglycemic therapy (70%), hypertriglyceridemia (65%), anemia (hemoglobin < 10 g/dL) (65%), fasting blood glucose > 140 mg/dL (on two separate occasions) (61%), hypercholesterolemia (57%), hyperlipidemia (34%), WBCs < 3000 cells/mcL (34%), serious bacterial infections (30%), magnesium < 1.2 mEq/L (24%), platelet count < 75,000 cells/mcL (19%), and other opportunistic infections (15%).

Other targeted treatment-emergent adverse reactions in tacrolimus-treated patients occurred at a rate of less than 15%, and include the following: Cushingoid features, impaired wound healing, hyperkalemia, Candida infection, and CMV infection/syndrome. Other less frequently observed adverse reactions in heart transplantation patients are described under the subsection “Less Frequently Reported Adverse Reactions (> 3% and < 15%) in Liver, Kidney and Heart Transplant Studies.”

New Onset Diabetes After Transplant

Kidney Transplantation

New Onset Diabetes After Transplant (NODAT) is defined as a composite of fasting plasma glucose ≥ 126 mg/dL, HbA1C ≥ 6%, insulin use ≥ 30 days, or oral hypoglycemic use. In a trial in kidney transplant patients (Study 2), NODAT was observed in 75% in the tacrolimus-treated and 61% in the NEORAL-treated patients without pre-transplant history of diabetes mellitus (Table 10) [see Clinical Studies (14.1)].

Table 10. Incidence of New Onset Diabetes After Transplant at 1 year in Kidney Transplant Recipients in a Phase 3 Trial (Study 2)

Parameter | Treatment Group
Parameter | Tacrolimus/MMF (N = 212) | NEORAL/MMF (N = 212)
NODAT | 112/150 (75%) | 93/152 (61%)
Fasting Plasma Glucose ≥ 126 mg/dL | 96/150 (64%) | 80/152 (53%)
HbA1C ≥ 6% | 59/150 (39%) | 28/152 (18%)
Insulin Use ≥ 30 days | 9/150 (6%) | 4/152 (3%)
Oral Hypoglycemic Use | 15/150 (10%) | 5/152 (3%)

In early trials of tacrolimus, Post-Transplant Diabetes Mellitus (PTDM) was evaluated with a more limited criterion of “use of insulin for 30 or more consecutive days with < 5-day gap” in patients without a prior history of insulin-dependent diabetes mellitus or non-insulin dependent diabetes mellitus. Data are presented in Tables 11 to 14. PTDM was reported in 20% of tacrolimus/Azathioprine (AZA)-treated kidney transplant patients without pre-transplant history of diabetes mellitus in a Phase 3 trial (Table 11). The median time to onset of PTDM was 68 days. Insulin dependence was reversible in 15% of these PTDM patients at one year and in 50% at 2 years post-transplant. African-American and Hispanic kidney transplant patients were at an increased risk of development of PTDM (Table 12).

Table 11. Incidence of Post-Transplant Diabetes Mellitus and Insulin Use at 2 Years in Kidney Transplant Recipients in a Phase 3 Trial using Azathioprine (AZA)

Status of PTDM* | Tacrolimus /AZA | CsA/AZA
Patients without pre-transplant history of diabetes mellitus | 151 | 151
New onset PTDM*, 1st Year | 30/151 (20%) | 6/151 (4%)
Still insulin-dependent at one year in those without prior history of diabetes | 25/151 (17%) | 5/151 (3%)
New onset PTDM* post 1 year | 1 | 0
Patients with PTDM* at 2 years | 16/151 (11%) | 5/151 (3%)

*Use of insulin for 30 or more consecutive days, with < 5-day gap, without a prior history of insulin-dependent diabetes mellitus or non-insulin dependent diabetes mellitus.

Table 12. Development of Post-Transplant Diabetes Mellitus by Race or Ethnicity and by Treatment Group During First Year Post Kidney Transplantation in a Phase 3 Trial

Patient Race | Patients Who Developed PTDM*
Patient Race | Tacrolimus | Cyclosporine
African-American | 15/41 (37%) | 3 (8%)
Hispanic | 5/17 (29%) | 1 (6%)
Caucasian | 10/82 (12%) | 1 (1%)
Other | 0/11 (0%) | 1 (10%)
Total | 30/151 (20%) | 6 (4%)

*Use of insulin for 30 or more consecutive days, with < 5-day gap, without a prior history of insulin-dependent diabetes mellitus or non-insulin dependent diabetes mellitus.

Liver Transplantation

Insulin-dependent PTDM was reported in 18% and 11% of tacrolimus-treated liver transplant patients and was reversible in 45% and 31% of these patients at 1 year post-transplant, in the U.S. and European randomized trials, respectively (Table 13). Hyperglycemia was associated with the use of tacrolimus in 47% and 33% of liver transplant recipients in the U.S. and European randomized trials, respectively, and may require treatment [see Adverse Reactions (6.1)].

Table 13. Incidence of Post-Transplant Diabetes Mellitus and Insulin Use at 1 Year in Liver Transplant Recipients

Status of PTDM* | US Trial |  | European Trial
Status of PTDM* | Tacrolimus | Cyclosporine | Tacrolimus | Cyclosporine
Patients at risk† | 239 | 236 | 239 | 249
New Onset PTDM* | 42 (18%) | 30 (13%) | 26 (11%) | 12 (5%)
Patients still on insulin at 1 year | 23 (10%) | 19 (8%) | 18 (8%) | 6 (2%)

*Use of insulin for 30 or more consecutive days, with < 5-day gap, without a prior history of insulin-dependent diabetes mellitus or non-insulin dependent diabetes mellitus.

†Patients without pre-transplant history of diabetes mellitus.

Heart Transplantation

Insulin-dependent PTDM was reported in 13% and 22% of tacrolimus-treated heart transplant patients receiving mycophenolate mofetil (MMF) or azathioprine (AZA) and was reversible in 30% and 17% of these patients at one year post-transplant, in the U.S. and European randomized trials, respectively (Table 14). Hyperglycemia, defined as two fasting plasma glucose levels ≥126 mg/dL, was reported with the use of tacrolimus plus MMF or AZA in 32% and 35% of heart transplant recipients in the U.S. and European randomized trials, respectively, and may require treatment [see Adverse Reactions (6.1)].

Table 14. Incidence of Post-Transplant Diabetes Mellitus and Insulin Use at 1 Year in Heart Transplant Recipients

Status of PTDM* | US Trial |  | European Trial
Status of PTDM* | Tacrolimus/MMF | Cyclosporine/MMF | Tacrolimus/AZA | Cyclosporine/AZA
Patients at risk† | 75 | 83 | 132 | 138
New Onset PTDM* | 10 (13%) | 6 (7%) | 29 (22%) | 5 (4%)
Patients still on insulin at 1 year‡ | 7 (9%) | 1 (1%) | 24 (18%) | 4 (3%)

*Use of insulin for 30 or more consecutive days without a prior history of insulin-dependent diabetes mellitus or non-insulin dependent diabetes mellitus.

†Patients without pre-transplant history of diabetes mellitus.

‡7 to 12 months for the U.S. trial.

Less Frequently Reported Adverse Reactions (> 3% and < 15%) in Liver, Kidney, and Heart Transplant Studies

The following adverse reactions were reported in either liver, kidney, and/or heart transplant recipients who were treated with tacrolimus in clinical trials.

- Nervous System: Abnormal dreams, agitation, amnesia, anxiety, confusion, convulsion, crying, depression, elevated mood, emotional lability, encephalopathy, hemorrhagic stroke, hallucinations, hypertonia, incoordination, monoparesis, myoclonus, nerve compression, nervousness, neuralgia, neuropathy, paralysis flaccid, psychomotor skills impaired, psychosis, quadriparesis, somnolence, thinking abnormal, vertigo, writing impaired
- Special Senses: Abnormal vision, amblyopia, ear pain, otitis media, tinnitus
- Gastrointestinal: Cholangitis, cholestatic jaundice, duodenitis, dysphagia, esophagitis, flatulence, gastritis, gastroesophagitis, gastrointestinal hemorrhage, GGT increase, GI disorder, GI perforation, hepatitis, hepatitis granulomatous, ileus, increased appetite, jaundice, liver damage, esophagitis ulcerative, oral moniliasis, pancreatic pseudocyst, stomatitis
- Cardiovascular: Abnormal ECG, angina pectoris, arrhythmia, atrial fibrillation, atrial flutter, bradycardia, cardiac fibrillation, cardiopulmonary failure, congestive heart failure, deep thrombophlebitis, echocardiogram abnormal, electrocardiogram QRS complex abnormal, electrocardiogram ST segment abnormal, heart failure, heart rate decreased, hemorrhage, hypotension, phlebitis, postural hypotension, syncope, tachycardia, thrombosis, vasodilatation
- Urogenital: Acute kidney failure, albuminuria, BK nephropathy, bladder spasm, cystitis, dysuria, hematuria, hydronephrosis, kidney failure, kidney tubular necrosis, nocturia, pyuria, toxic nephropathy, urge incontinence, urinary frequency, urinary incontinence, urinary retention, vaginitis
- Metabolic/Nutritional: Acidosis, alkaline phosphatase increased, alkalosis, ALT (SGPT) increased, AST (SGOT) increased, bicarbonate decreased, bilirubinemia, dehydration, GGT increased, gout, healing abnormal, hypercalcemia, hypercholesterolemia, hyperphosphatemia, hyperuricemia, hypervolemia, hypocalcemia, hypoglycemia, hyponatremia, hypoproteinemia, lactic dehydrogenase increased, weight gain
- Endocrine: Cushing’s syndrome
- Hemic/Lymphatic: Coagulation disorder, ecchymosis, hematocrit increased, hypochromic anemia, leukocytosis, polycythemia, prothrombin decreased, serum iron decreased
- Miscellaneous: Abdomen enlarged, abscess, accidental injury, allergic reaction, cellulitis, chills, fall, flu syndrome, generalized edema, hernia, mobility decreased, peritonitis, photosensitivity reaction, sepsis, temperature intolerance, ulcer
- Musculoskeletal: Arthralgia, cramps, generalized spasm, leg cramps, myalgia, myasthenia, osteoporosis
- Respiratory: Asthma, emphysema, hiccups, lung function decreased, pharyngitis, pneumonia, pneumothorax, pulmonary edema, rhinitis, sinusitis, voice alteration
- Skin: Acne, alopecia, exfoliative dermatitis, fungal dermatitis, herpes simplex, herpes zoster, hirsutism, neoplasm skin benign, skin discoloration, skin ulcer, sweating

6.2 Postmarketing Experience

The following adverse reactions have been reported from worldwide marketing experience with tacrolimus. Because these reactions are reported voluntarily from a population of uncertain size, it is not always possible to reliably estimate their frequency or establish a causal relationship to drug exposure. Decisions to include these reactions in labeling are typically based on one or more of the following factors: (1) seriousness of the reaction, (2) frequency of the reporting, or (3) strength of causal connection to the drug.

Other reactions include:

- Cardiovascular: Atrial fibrillation, atrial flutter, cardiac arrhythmia, cardiac arrest, electrocardiogram T wave abnormal, flushing, myocardial infarction, myocardial ischemia, pericardial effusion, QT prolongation, Torsades de pointes, venous thrombosis deep limb, ventricular extrasystoles, ventricular fibrillation, myocardial hypertrophy
- Gastrointestinal: Bile duct stenosis, colitis, enterocolitis, gastroenteritis, gastroesophageal reflux disease, hepatic cytolysis, hepatic necrosis, hepatotoxicity, impaired gastric emptying, liver fatty, mouth ulceration, pancreatitis hemorrhagic, pancreatitis necrotizing, stomach ulcer, veno-occlusive liver disease
- Hemic/Lymphatic: Agranulocytosis, disseminated intravascular coagulation, hemolytic anemia, neutropenia, febrile neutropenia, pancytopenia, thrombocytopenic purpura, thrombotic thrombocytopenic purpura, pure red cell aplasia, thrombotic microangiopathy
- Infections: Cases of progressive multifocal leukoencephalopathy (PML), sometimes fatal; polyoma virus-associated nephropathy (PVAN) including graft loss
- Metabolic/Nutritional: Glycosuria, increased amylase including pancreatitis, weight decreased
- Miscellaneous: Feeling hot and cold, feeling jittery, hot flushes, multi-organ failure, primary graft dysfunction
- Musculoskeletal and Connective Tissue Disorders: Pain in extremity including Calcineurin-Inhibitor Induced Pain Syndrome (CIPS)
- Nervous System: Carpal tunnel syndrome, cerebral infarction, hemiparesis, leukoencephalopathy, mental disorder, mutism, posterior reversible encephalopathy syndrome (PRES), progressive multifocal leukoencephalopathy (PML), quadriplegia, speech disorder, syncope
- Respiratory: Acute respiratory distress syndrome, interstitial lung disease, lung infiltration, respiratory distress, respiratory failure
- Skin: Stevens-Johnson syndrome, toxic epidermal necrolysis
- Special Senses: Blindness, optic neuropathy, blindness cortical, hearing loss including deafness, photophobia
- Urogenital: Acute renal failure, cystitis hemorrhagic, hemolytic-uremic syndrome

7 DRUG INTERACTIONS

7.1 Mycophenolic Acid

When tacrolimus is prescribed with a given dose of a mycophenolic acid (MPA) product, exposure to MPA is higher with tacrolimus co-administration than with cyclosporine co-administration with MPA, because cyclosporine interrupts the enterohepatic recirculation of MPA while tacrolimus does not. Monitor for MPA-associated adverse reactions and reduce the dose of concomitantly administered mycophenolic acid products as needed.

7.2 Effects of Other Drugs on Tacrolimus

Table 15 displays the effects of other drugs on tacrolimus.

Table 15: Effects of Other Drugs/Substances on Tacrolimus*

Drug/Substance Class or Name | Drug Interaction Effect | Recommendations
Grapefruit or grapefruit juice† | May increase tacrolimus whole blood trough concentrations and increase the risk of serious adverse reactions (e.g., neurotoxicity, QT prolongation) [see Warnings and Precautions (5.6, 5.11, 5.12)]. | Avoid grapefruit or grapefruit juice.
Strong CYP3A Inducers‡:; Antimycobacterials (e.g., rifampin, rifabutin), anticonvulsants (e.g., phenytoin, carbamazepine and phenobarbital), St John’s Wort | May decrease tacrolimus whole blood trough concentrations and increase the risk of rejection [see Warnings and Precautions (5.11)]. | Increase tacrolimus dose and monitor tacrolimus whole blood trough concentrations [see Dosage and Administration (2.2, 2.6) and Clinical Pharmacology (12.3)].
Strong CYP3A Inhibitors‡:; Protease inhibitors (e.g., nelfinavir, telaprevir, boceprevir, ritonavir), azole antifungals (e.g., voriconazole, posaconazole, itraconazole, ketoconazole), antibiotics (e.g., clarithromycin, troleandomycin, chloramphenicol), nefazodone, letermovir, Schisandra sphenanthera extracts | May increase tacrolimus whole blood trough concentrations and increase the risk of serious adverse reactions (e.g., neurotoxicity, QT prolongation). A rapid, sharp rise in tacrolimus levels may occur early, despite an immediate reduction of tacrolimus dose [see Warnings and Precautions (5.6, 5.11, 5.12)]. | Reduce tacrolimus dose (for voriconazole and posaconazole, give one-third of the original dose) and adjust dose based on tacrolimus whole blood trough concentrations [see Dosage and Administration (2.2, 2.6) and Clinical Pharmacology (12.3)]. Early and frequent monitoring of tacrolimus whole blood trough levels should start within 1 to 3 days and continue monitoring as necessary [see Warnings and Precautions (5.11)].
Mild or Moderate CYP3A Inhibitors:; Clotrimazole, antibiotics (e.g., erythromycin, fluconazole), calcium channel blockers (e.g., verapamil, diltiazem, nifedipine, nicardipine), amiodarone, danazol, ethinyl estradiol, cimetidine, lansoprazole and omeprazole | May increase tacrolimus whole blood trough concentrations and increase the risk of serious adverse reactions (e.g., neurotoxicity, QT prolongation) [see Warnings and Precautions (5.6, 5.11, 5.12)]. | Monitor tacrolimus whole blood trough concentrations and reduce tacrolimus dose if needed [see Dosage and Administration (2.2, 2.6) and Clinical Pharmacology (12.3)].
Other drugs, such as:; Magnesium and aluminum hydroxide antacids Metoclopramide | May increase tacrolimus whole blood trough concentrations and increase the risk of serious adverse reactions (e.g., neurotoxicity, QT prolongation) [see Warnings and Precautions (5.6, 5.11, 5.12)]. | Monitor tacrolimus whole blood trough concentrations and reduce tacrolimus dose if needed [see Dosage and Administration (2.2, 2.6) and Clinical Pharmacology (12.3)].
Mild or Moderate CYP3A Inducers Methylprednisolone, prednisone | May decrease tacrolimus whole blood trough concentrations. | Monitor tacrolimus whole blood trough concentrations and adjust tacrolimus dose if needed [see Dosage and Administration (2.2, 2.6)].
Caspofungin | May decrease tacrolimus whole blood trough concentrations. | Monitor tacrolimus whole blood trough concentrations and adjust tacrolimus dose if needed [see Dosage and Administration (2.2, 2.6)].

*tacrolimus dosage adjustment recommendation based on observed effect of coadministered drug on tacrolimus exposures [see Clinical Pharmacology (12.3)], literature reports of altered tacrolimus exposures, or the other drug’s known CYP3A inhibitor/inducer status.

†High dose or double strength grapefruit juice is a strong CYP3A inhibitor; low dose or single strength grapefruit juice is a moderate CYP3A inhibitor.

‡Strong CYP3A inhibitor/inducer, based on reported effect on exposures to tacrolimus along with supporting in vitro CYP3A inhibitor/inducer data, or based on drug-drug interaction studies with midazolam (sensitive CYP3A probe substrate).

Direct Acting Antiviral (DAA) Therapy

The pharmacokinetics of tacrolimus may be impacted by changes in liver function during DAA therapy, related to clearance of HCV virus. Close monitoring and potential dose adjustment of tacrolimus is warranted to ensure continued efficacy and safety [see Dosage and Administration (2.2, 2.6)].

7.3 Cannabidiol

The blood levels of tacrolimus may increase upon concomitant use with cannabidiol. When cannabidiol and tacrolimus are coadministered, closely monitor for an increase in tacrolimus blood levels and for adverse reactions suggestive of tacrolimus toxicity. A dose reduction of tacrolimus should be considered as needed when tacrolimus is coadministered with cannabidiol [see Dosage and Administration (2.2,2.6) and Warnings and Precautions (5.17)].

8 USE IN SPECIFIC POPULATIONS

8.1 Pregnancy

Pregnancy Exposure Registry

There is a pregnancy registry that monitors pregnancy outcomes in women exposed to tacrolimus during pregnancy. The Transplantation Pregnancy Registry International (TPRI) is a voluntary pregnancy exposure registry that monitors outcomes of pregnancy in female transplant recipients and those fathered by male transplant recipients exposed to immunosuppressants including tacrolimus. Healthcare providers are encouraged to advise their patients to register by contacting the Transplantation Pregnancy Registry International at 1-877-955-6877 or https://www.transplantpregnancyregistry.org/.

Risk Summary

Tacrolimus can cause fetal harm when administered to a pregnant woman. Data from postmarketing surveillance and TPRI suggest that infants exposed to tacrolimus in utero are at a risk of prematurity, birth defects/congenital anomalies, low birth weight, and fetal distress [see Human Data]. Advise pregnant women of the potential risk to the fetus. Administration of oral tacrolimus to pregnant rabbits and rats throughout the period of organogenesis was associated with maternal toxicity/lethality, and an increased incidence of abortion, malformation and embryofetal death at clinically relevant doses (0.5 to 6.9 times the recommended clinical dose range [0.2 mg/kg/day to 0.075 mg/kg/day], on a mg/m^2 basis). Administration of oral tacrolimus to pregnant rats after organogenesis and throughout lactation produced maternal toxicity, effects on parturition, reduced pup viability and reduced pup weight at clinically relevant doses (0.8 to 6.9 times the recommended clinical dose range, on a mg/m^2 basis). Administration of oral tacrolimus to rats prior to mating, and throughout gestation and lactation produced maternal toxicity/lethality, marked effects on parturition, embryofetal loss, malformations, and reduced pup viability at clinically relevant doses (0.8 to 6.9 times the recommended clinical dose range, on a mg/m^2 basis). Interventricular septal defects, hydronephrosis, craniofacial malformations and skeletal effects were observed in offspring that died [see Animal Data].

The background risk of major birth defects and miscarriage in the indicated population is unknown. In the U.S. general population, the estimated background risk of major birth defects and miscarriage in clinically recognized pregnancies is 2 to 4% and 15 to 20%, respectively.

Clinical Considerations

Disease-Associated Maternal and/or Embryo-Fetal Risk

Risks during pregnancy are increased in organ transplant recipients.

The risk of premature delivery following transplantation is increased. Pre-existing hypertension and diabetes confer additional risk to the pregnancy of an organ transplant recipient. Pre-gestational and gestational diabetes are associated with birth defects/congenital anomalies, hypertension, low birth weight and fetal death.

Cholestasis of pregnancy (COP) was reported in 7% of liver or liver-kidney (LK) transplant recipients, compared with approximately 1% of pregnancies in the general population. However, COP symptoms resolved postpartum and no long‑term effects on the offspring were reported.

Maternal Adverse Reactions

Tacrolimus may increase hyperglycemia in pregnant women with diabetes (including gestational diabetes). Monitor maternal blood glucose levels regularly [see Warnings and Precautions (5.4)].

Tacrolimus may exacerbate hypertension in pregnant women and increase pre-eclampsia. Monitor and control blood pressure [see Warnings and Precautions (5.7, 5.8)].

Fetal/Neonatal Adverse Reactions

Renal dysfunction, transient neonatal hyperkalemia and low birth weight have been reported at the time of delivery in infants of mothers taking tacrolimus.

Labor or Delivery

There is an increased risk for premature delivery (< 37 weeks) following transplantation and maternal exposure to tacrolimus.

Data

Human Data

There are no adequate and well controlled studies on the effects of tacrolimus in human pregnancy.

Safety data from the TPRI and postmarketing surveillance suggest infants exposed to tacrolimus in utero have an increased risk for miscarriage, pre-term delivery (< 37 weeks), low birth weight (< 2500 g), birth defects/congenital anomalies and fetal distress.

TPRI reported 450 and 241 total pregnancies in kidney and liver transplant recipients exposed to tacrolimus, respectively. The TPRI pregnancy outcomes are summarized in Table 16. In the table below, the number of recipients exposed to tacrolimus concomitantly with mycophenolic acid (MPA) products during the preconception and first trimester periods is high (27% and 29% for renal and liver transplant recipients, respectively). Because MPA products may also cause birth defects, the birth defect rate may be confounded and this should be taken into consideration when reviewing the data, particularly for birth defects. Birth defects observed include cardiac malformations, craniofacial malformations, renal/urogenital disorders, skeletal abnormalities, neurological abnormalities and multiple malformations.

Table 16. TPRI Reported Pregnancy Outcomes in Transplant Recipients with Exposure to Tacrolimus

 | Kidney | Liver
Pregnancy Outcomes* | 462 | 253
Miscarriage | 24.5% | 25%
Live births | 331 | 180
Pre-term delivery (< 37 weeks) | 49% | 42%
Low birth weight (< 2500 g) | 42% | 30%
Birth defects | 8%† | 5%

*Includes multiple births and terminations.

†Birth defect rate confounded by concomitant MPA products exposure in over half of offspring with birth defects.

Additional information reported by TPRI in pregnant transplant patients receiving tacrolimus included diabetes during pregnancy in 9% of kidney recipients and 13% of liver recipients, and hypertension during pregnancy in 53% of kidney recipients and 16.2% of liver recipients.

Animal Data

Administration of oral tacrolimus to pregnant rabbits throughout organogenesis produced maternal toxicity and abortion at 0.32 mg/kg (0.5 to 1.4 times the recommended clinical dose range [0.2 to 0.075 mg/kg/day], on a mg/m^2 basis). At 1 mg/kg (1.6 to 4.3 times the recommended clinical dose range), embryofetal lethality and fetal malformations (ventricular hypoplasia, interventricular septal defect, bulbous aortic arch, stenosis of ductus arteriosus, omphalocele, gallbladder agenesis, skeletal anomalies) were observed. Administration of 3.2 mg/kg oral tacrolimus (2.6 to 6.9 times the recommended clinical dose range) to pregnant rats throughout organogenesis produced maternal toxicity/lethality, embryofetal lethality and decreased fetal body weight in the offspring of C-sectioned dams; and decreased pup viability and interventricular septal defect in offspring of dams that delivered.

In a peri-/postnatal development study, oral administration of tacrolimus to pregnant rats during late gestation (after organogenesis) and throughout lactation produced maternal toxicity, effects on parturition, and reduced pup viability at 3.2 mg/kg (2.6 to 6.9 times the recommended clinical dose range); among these pups that died early, an increased incidence of kidney hydronephrosis was observed. Reduced pup weight was observed at 1 mg/kg (0.8 to 2.2 times the recommended clinical dose range).

Administration of oral tacrolimus to rats prior to mating, and throughout gestation and lactation, produced maternal toxicity/lethality, embryofetal loss and reduced pup viability at 3.2 mg/kg (2.6 to 6.9 times the recommended clinical dose range). Interventricular septal defects, hydronephrosis, craniofacial malformations and skeletal effects were observed in offspring that died. Effects on parturition (incomplete delivery of nonviable pups) were observed at 1 mg/kg (0.8 to 2.2 times the recommended clinical dose range) [see Nonclinical Toxicology (13.1)].

8.2 Lactation

Risk Summary

Controlled lactation studies have not been conducted in humans; however, tacrolimus has been reported to be present in human milk. The effects of tacrolimus on the breastfed infant, or on milk production have not been assessed. Tacrolimus is excreted in rat milk and in peri-/postnatal rat studies; exposure to tacrolimus during the postnatal period was associated with developmental toxicity in the offspring at clinically relevant doses [see Use in Specific Populations (8.1) and Nonclinical Toxicology (13.1)].

The developmental and health benefits of breastfeeding should be considered along with the mother’s clinical need for tacrolimus and any potential adverse effects on the breastfed child from tacrolimus or from the underlying maternal condition.

8.3 Females and Males of Reproductive Potential

Contraception

Tacrolimus can cause fetal harm when administered to pregnant women. Advise female and male patients of reproductive potential to speak to their healthcare provider on family planning options including appropriate contraception prior to starting treatment with tacrolimus [see Use in Specific Populations (8.1) and Nonclinical Toxicology (13.1)].

Infertility

Based on findings in animals, male and female fertility may be compromised by treatment with tacrolimus [see Nonclinical Toxicology (13.1)].

8.4 Pediatric Use

Safety and effectiveness have been established in pediatric liver, kidney and heart transplant patients.

Liver Transplantation

Safety and efficacy in pediatric liver transplant patients less than 16 years of age are based on evidence from active controlled studies that included 56 pediatric patients, 31 of which received tacrolimus. Additionally, 122 pediatric patients were studied in an uncontrolled trial of tacrolimus in living related donor liver transplantation. Pediatric patients generally required higher doses of tacrolimus to maintain blood trough concentrations of tacrolimus similar to adult patients [see Dosage and Administration (2.3), Adverse Reactions (6.1), Clinical Pharmacology (12.3) and Clinical Studies (14.2)].

Kidney and Heart Transplantation

Use of tacrolimus capsules in pediatric kidney and heart transplant patients is supported by adequate and well-controlled studies and pharmacokinetic data in adult kidney and heart transplant patients with additional pharmacokinetic data in pediatric kidney and heart transplant patients and safety data in pediatric liver transplant patients [see Dosage and Administration (2.3) and Clinical Pharmacology (12.3)].

8.5 Geriatric Use

Clinical trials of tacrolimus did not include sufficient numbers of subjects aged 65 and over to determine whether they respond differently from younger subjects. Other reported clinical experience has not identified differences in responses between the elderly and younger patients. In general, dose selection for an elderly patient should be cautious, usually starting at the low end of the dosing range, reflecting the greater frequency of decreased hepatic, renal, or cardiac function, and of concomitant disease or other drug therapy.

8.6 Renal Impairment

The pharmacokinetics of tacrolimus in patients with renal impairment was similar to that in healthy volunteers with normal renal function. However, consideration should be given to dosing tacrolimus at the lower end of the therapeutic dosing range in patients who have received a liver or heart transplant and have pre-existing renal impairment. Further reductions in dose below the targeted range may be required [see Dosage and Administration (2.4) and Clinical Pharmacology (12.3)].

8.7 Hepatic Impairment

The mean clearance of tacrolimus was substantially lower in patients with severe hepatic impairment (mean Child-Pugh score: > 10) compared to healthy volunteers with normal hepatic function. Close monitoring of tacrolimus trough concentrations is warranted in patients with hepatic impairment [see Clinical Pharmacology (12.3)].

The use of tacrolimus in liver transplant recipients experiencing post-transplant hepatic impairment may be associated with increased risk of developing renal insufficiency related to high whole blood trough concentrations of tacrolimus. These patients should be monitored closely and dosage adjustments should be considered. Some evidence suggests that lower doses should be used in these patients [see Dosage and Administration (2.5) and Clinical Pharmacology (12.3)].

8.8 Race or Ethnicity

African-American patients may need to be titrated to higher dosages to attain comparable trough concentrations compared to Caucasian patients [see Dosage and Administration (2.2) and Clinical Pharmacology (12.3)].

African-American and Hispanic patients are at increased risk for new onset diabetes after transplant. Monitor blood glucose concentrations and treat appropriately [see Warnings and Precautions (5.4)].

10 OVERDOSAGE

Limited overdosage experience is available. Acute overdosages of up to 30 times the intended dose have been reported. Almost all cases have been asymptomatic and all patients recovered with no sequelae. Acute overdosage was sometimes followed by adverse reactions consistent with those reported with the use of tacrolimus [see Adverse Reactions (6.1, 6.2)], including tremors, abnormal renal function, hypertension, and peripheral edema; in one case of acute overdosage, transient urticaria and lethargy were observed. Based on the poor aqueous solubility and extensive erythrocyte and plasma protein binding, it is anticipated that tacrolimus is not dialyzable to any significant extent; there is no experience with charcoal hemoperfusion. The oral use of activated charcoal has been reported in treating acute overdoses, but experience has not been sufficient to warrant recommending its use. General supportive measures and treatment of specific symptoms should be followed in all cases of overdosage.

11 DESCRIPTION

Tacrolimus, USP previously known as FK506, is the active ingredient in Tacrolimus Capsules, USP. Tacrolimus, USP is a calcineurin-inhibitor immunosuppressant produced by Streptomyces tsukubaensis. Chemically, tacrolimus, USP is designated as (-)-(3S,4R,5S,8R,9E,12S,14S,15R,16S,18R,19R,26aS)-8-Allyl-5,6,8,11,12,13,14,15,16,17,18,19,24,25,26,26a-hexadecahydro-5,19-dihydroxy-3-[(E)-2-[(1R,3R,4R)-4-hydroxy-3-methoxy cyclohexyl]-1-methylvinyl]-14,16-dimethoxy-4,10,12,18-tetramethyl-15,19-epoxy-3H-pyrido[2,1-c][1,4]oxaazacyclotricosine-1,7,20,21(4H,23H)-tetrone,monohydrate.

The chemical structure of tacrolimus, USP is:

Tacrolimus, USP has an empirical formula of C44H69NO12•H2O and a formula weight of 822.03 g/mol. Tacrolimus, USP appears as white to off-white powder. It is soluble in acetone, chloroform and ethyl acetate; insoluble in water.

Tacrolimus Capsules, USP are available for oral administration as capsules containing the equivalent of 0.5 mg, 1 mg or 5 mg of anhydrous tacrolimus, USP. Inactive ingredients include croscarmellose sodium, hypromellose, lactose monohydrate, and magnesium stearate. The 0.5 mg capsule shell contains D&C Yellow 10, FD&C Red 40, FD&C Blue 1, gelatin, shellac, sodium hydroxide, povidone and titanium dioxide. The 1 mg capsule shell contains FD&C Red 40, gelatin, shellac, sodium hydroxide, povidone and titanium dioxide. The 5 mg capsule shell contains gelatin, D&C Yellow 10, FD&C Blue 1, FD&C Red 40, potassium hydroxide, shellac and titanium dioxide.

FDA approved dissolution test specifications differ from USP.

12 CLINICAL PHARMACOLOGY

12.1 Mechanism of Action

Tacrolimus binds to an intracellular protein, FKBP-12. A complex of tacrolimus-FKBP-12, calcium, calmodulin, and calcineurin (a ubiquitous mammalian intracellular enzyme) is then formed, after which the phosphatase activity of calcineurin is inhibited. Such inhibition prevents the dephosphorylation and translocation of various factors such as the nuclear factor of activated T-cells (NF-AT), and nuclear factor kappa-light-chain enhancer of activated B-cells (NF-κB).

Tacrolimus inhibits the expression and/or production of several cytokines that include interleukin (IL)-1 beta, IL-2, IL-3, IL-4, IL-5, IL-6, IL-8, IL-10, gamma interferon, tumor necrosis factor-alpha, and granulocyte macrophage colony-stimulating factor. Tacrolimus also inhibits IL-2 receptor expression and nitric oxide release, induces apoptosis and production of transforming growth factor beta that can lead to immunosuppressive activity. The net result is the inhibition of T-lymphocyte activation and proliferation, as well as T-helper-cell-dependent B-cell response (i.e., immunosuppression).

12.3 Pharmacokinetics

Tacrolimus activity is primarily due to the parent drug. The pharmacokinetic parameters (mean ± S.D.) of tacrolimus have been determined following intravenous (IV) and/or oral (PO) administration in healthy volunteers, and in kidney transplant, liver transplant, and heart transplant patients (Table 17).

Table 17. Pharmacokinetics Parameters (mean ± S.D.) of Tacrolimus in Healthy Volunteers and Patients

Population | N | Route (Dose) | Parameters
Population | N | Route (Dose) | Cmax (ng/mL) | Tmax (hr) | AUC (ng•hr/mL) | t1/2 (hr) | CL (L/hr/kg) | V (L/kg)
Healthy Volunteers | 8 | IV; (0.025 mg/kg/4 hr) | * | * | 652† ± 156 | 34.2 ± 7.7 | 0.040 ± 0.009 | 1.91 ± 0.31
Healthy Volunteers | 16 | PO; (5 mg) (capsules) | 28.8 ± 8.9 | 1.5 ± 0.7 | 266† ± 95 | 32.3 ± 8.8 | ‡ | ‡
Kidney Transplant Patients | 26 | IV; (0.02 mg/kg/12 hr) | * | * | 294† ± 262 | 18.8 ± 16.7 | 0.083 ± 0.050 | 1.41 ± 0.66
Kidney Transplant Patients | 26 | PO; (0.2 mg/kg/day) | 19.2 ± 10.3 | 3 | 203† ± 42 | ‡ | ‡ | ‡
Kidney Transplant Patients | 26 | PO; (0.3 mg/kg/day) | 24.2 ± 15.8 | 1.5 | 288† ± 93 | ‡ | ‡ | ‡
Liver Transplant Patients | 17 | IV; (0.05 mg/kg/12 hr) | * | * | 3300† ± 2130 | 11.7 ± 3.9 | 0.053 ± 0.017 | 0.85 ± .30
Liver Transplant Patients | 17 | PO; (0.3 mg/kg/day) | 68.5 ± 30 | 2.3 ± 1.5 | 519† ± 179 | ‡ | ‡ | ‡
Heart Transplant Patients | 11 | IV; (0.01 mg/kg/day as a continuous infusion) | * | * | 954§ ± 334 | 23.6 ± 9.22 | 0.051 ± 0.015 | ‡
Heart Transplant Patients | 11 | PO; (0.075 mg/kg/day)¶ | 14.7 + 7.79 | 2.1; [0.5 to 6]# | 82.7Þ ± 63.2 | * | ‡ | ‡
Heart Transplant Patients | 14 | PO; (0.15 mg/kg/day)¶ | 24.5 ± 13.7 | 1.5; [0.4 to 4]# | 142Þ ± 116 | * | ‡ | ‡

* Not applicable

† AUC0 to inf

‡ Not available

§ AUC0 to t

¶ Determined after the first dose

# Median [range]

Þ AUC0 to 12

Due to intersubject variability in tacrolimus pharmacokinetics, individualization of the dosing regimen is necessary for optimal therapy [see Dosage and Administration (2.6)]. Pharmacokinetic data indicate that whole blood concentrations rather than plasma concentrations serve as the more appropriate sampling compartment to describe tacrolimus pharmacokinetics.

Absorption

Absorption of tacrolimus from the gastrointestinal tract after oral administration is incomplete and variable. The absolute bioavailability of tacrolimus was 17 ± 10% in adult kidney transplant patients (N = 26), 22 ± 6% in adult liver transplant patients (N = 17), 23 ± 9% in adult heart transplant patients (N = 11) and 18 ± 5% in healthy volunteers (N = 16).

A single dose trial conducted in 32 healthy volunteers established the bioequivalence of the 1 mg and 5 mg capsules. Another single dose trial in 32 healthy volunteers established the bioequivalence of the 0.5 mg and 1 mg capsules. Tacrolimus maximum blood concentrations (Cmax) and area under the curve (AUC) appeared to increase in a dose- proportional fashion in 18 fasted healthy volunteers receiving a single oral dose of 3, 7, and 10 mg.

In 18 kidney transplant patients, tacrolimus trough concentrations from 3 to 30 ng/mL measured at 10 to 12 hours post-dose (Cmin) correlated well with the AUC (correlation coefficient 0.93). In 24 liver transplant patients over a concentration range of 10 to 60 ng/mL, the correlation coefficient was 0.94. In 25 heart transplant patients over a concentration range of 2 to 24 ng/mL, the correlation coefficient was 0.89 after an oral dose of 0.075 or 0.15 mg/kg/day at steady-state.

If pediatric patients are converted between formulations, therapeutic drug monitoring must be performed and dose adjustments made to ensure that systemic exposure to tacrolimus is maintained.

Food Effects

The rate and extent of tacrolimus absorption were greatest under fasted conditions. The presence and composition of food decreased both the rate and extent of tacrolimus absorption when administered to 15 healthy volunteers.

The effect was most pronounced with a high-fat meal (848 kcal, 46% fat): mean AUC and Cmax were decreased 37% and 77%, respectively; Tmax was lengthened 5-fold. A high-carbohydrate meal (668 kcal, 85% carbohydrate) decreased mean AUC and mean Cmax by 28% and 65%, respectively.

In healthy volunteers (N = 16), the time of the meal also affected tacrolimus bioavailability. When given immediately following the meal, mean Cmax was reduced 71%, and mean AUC was reduced 39%, relative to the fasted condition. When administered 1.5 hours following the meal, mean Cmax was reduced 63%, and mean AUC was reduced 39%, relative to the fasted condition.

In 11 liver transplant patients, tacrolimus capsules administered 15 minutes after a high fat (400 kcal, 34% fat) breakfast, resulted in decreased AUC (27 ± 18%) and Cmax (50 ± 19%), as compared to a fasted state.

Tacrolimus capsules should be taken consistently every day either with or without food because the presence and composition of food decreases the bioavailability of tacrolimus capsules [see Dosage and Administration (2.1)].

Distribution

The plasma protein binding of tacrolimus is approximately 99% and is independent of concentration over a range of 5 to 50 ng/mL. Tacrolimus is bound mainly to albumin and alpha-1-acid glycoprotein, and has a high level of association with erythrocytes. The distribution of tacrolimus between whole blood and plasma depends on several factors, such as hematocrit, temperature at the time of plasma separation, drug concentration, and plasma protein concentration. In a U.S. trial, the ratio of whole blood concentration to plasma concentration averaged 35 (range 12 to 67).

Elimination

Metabolism

Tacrolimus is extensively metabolized by the mixed-function oxidase system, primarily the cytochrome P-450 system (CYP3A4 and CYP3A5). A metabolic pathway leading to the formation of 8 possible metabolites has been proposed. Demethylation and hydroxylation were identified as the primary mechanisms of biotransformation in vitro. The major metabolite identified in incubations with human liver microsomes is 13-demethyl tacrolimus. In in vitro studies, a 31-demethyl metabolite has been reported to have the same activity as tacrolimus.

Excretion

The mean clearance following IV administration of tacrolimus is 0.040, 0.083, 0.053, and 0.051 L/hr/kg in healthy volunteers, adult kidney transplant patients, adult liver transplant patients, and adult heart transplant patients, respectively. In man, less than 1% of the dose administered is excreted unchanged in urine.

In a mass balance study of IV-administered radiolabeled tacrolimus to 6 healthy volunteers, the mean recovery of radiolabel was 77.8 ± 12.7%. Fecal elimination accounted for 92.4 ± 1% and the elimination half-life based on radioactivity was 48.1 ± 15.9 hours whereas it was 43.5 ± 11.6 hours based on tacrolimus concentrations. The mean clearance of radiolabel was 0.029 ± 0.015 L/hr/kg and clearance of tacrolimus was 0.029 ± 0.009 L/hr/kg. When administered PO, the mean recovery of the radiolabel was 94.9 ± 30.7%. Fecal elimination accounted for 92.6 ± 30.7%, urinary elimination accounted for 2.3 ± 1.1% and the elimination half-life based on radioactivity was 31.9 ± 10.5 hours whereas it was 48.4 ± 12.3 hours based on tacrolimus concentrations. The mean clearance of radiolabel was 0.226 ± 0.116 L/hr/kg and clearance of tacrolimus was 0.172 ± 0.088 L/hr/kg.

Specific Populations

Pediatric Patients

Tacrolimus capsules Pharmacokinetics in Pediatric Patients

Pharmacokinetics of tacrolimus have been studied in liver transplantation patients, 0.7 to 13.2 years of age. Following IV administration of a 0.037 mg/kg/day dose to 12 pediatric patients, mean terminal half-life, volume of distribution and clearance were 11.5 ± 3.8 hours, 2.6 ± 2.1 L/kg and 0.138 ± 0.071 L/hr/kg, respectively. Following oral administration to

9 patients, mean AUC and Cmax were 337 ± 167 ng·hr/mL and 48.4 ± 27.9 ng/mL, respectively. The absolute bioavailability was 31 ± 24%.

Pharmacokinetics of tacrolimus have also been studied in kidney transplantation patients, 8.2 ± 2.4 years of age. Following IV infusion of a 0.06 mg/kg/day to 12 pediatric patients (8 male and 4 female), mean terminal half-life and clearance were 10.2 ± 5 hours and 0.12 ± 0.04 L/hr/kg, respectively. Following oral administration to the same patients, mean AUC and Cmax were 181 ± 65 ng·hr/mL and 30 ± 11 ng/mL, respectively. The absolute bioavailability was 19 ± 14%.

Whole blood trough concentrations from 31 patients less than 12 years old showed that pediatric patients needed higher doses than adults to achieve similar tacrolimus trough concentrations [see Dosage and Administration (2.3)].

Renal and Hepatic Impaired Patients

The mean pharmacokinetic parameters for tacrolimus following single administrations to adult patients with renal and hepatic impairment are given in Table 19.

Table 19. Pharmacokinetics in Renal and Hepatic Impaired Adult Patients

Population (No. of Patients) | Dose | AUC0 to t (ng·hr/mL) | t1/2 (hr) | V (L/kg) | CI (L/hr/kg)
Renal Impairment; (n = 12) | 0.02 mg/kg/4hr; IV | 393 ± 123; (t = 60 hr) | 26.3 ± 9.2 | 1.07 ± 0.20 | 0.038 ± 0.014
Mild Hepatic Impairment; (n = 6) | 0.02 mg/kg/4hr; IV | 367 ± 107; (t = 72 hr) | 60.6 ± 43.8; Range: 27.8 to 141 | 3.1 ± 1.6 | 0.042 ± 0.02
Mild Hepatic Impairment; (n = 6) | 7.7 mg; PO | 488 ± 320; (t = 72 hr) | 66.1 ± 44.8; Range: 29.5 to 138 | 3.7 ± 4.7* | 0.034 ± 0.019*
Severe Hepatic Impairment; (n = 6, IV) | 0.02 mg/kg/4hr; IV (n = 2) | 762 ± 204; (t = 120 hr) | 198 ± 158; Range: 81 to 436 | 3.9 ± 1 | 0.017 ± 0.013
Severe Hepatic Impairment; (n = 6, IV) | 0.01 mg/kg/8hr; IV (n = 4) | 289 ± 117; (t = 144 hr) | 198 ± 158; Range: 81 to 436 | 3.9 ± 1 | 0.017 ± 0.013
(n = 5, PO)† | 8 mg; PO (n = 1) | 658; (t = 120 hr) | 119 ± 35; Range: 85 to 178 | 3.1 ± 3.4* | 0.016 ± 0.011*
(n = 5, PO)† | 5 mg; PO (n = 4); 4 mg; PO (n = 1) | 533 ± 156; (t = 144 hr) | 119 ± 35; Range: 85 to 178 | 3.1 ± 3.4* | 0.016 ± 0.011*

*Corrected for bioavailability

†1 patient did not receive the PO dose

Patients with Renal Impairment

Tacrolimus pharmacokinetics, following a single IV administration, were determined in 12 patients (7 not on dialysis and 5 on dialysis, serum creatinine of 3.9 ± 1.6 and 12 ± 2.4 mg/dL, respectively) prior to their kidney transplant. The pharmacokinetic parameters obtained were similar for both groups. The mean clearance of tacrolimus in patients with renal dysfunction was similar to that in normal volunteers (Table 19) [see Dosage and Administration (2.2) and Use in Specific Populations (8.6)].

Patients with Hepatic Impairment

Tacrolimus pharmacokinetics have been determined in six patients with mild hepatic dysfunction (mean Pugh score: 6.2) following single IV and oral administrations. The mean clearance of tacrolimus in patients with mild hepatic dysfunction was not substantially different from that in normal volunteers (see previous table). Tacrolimus pharmacokinetics were studied in 6 patients with severe hepatic dysfunction (mean Pugh score: > 10). The mean clearance was substantially lower in patients with severe hepatic dysfunction, irrespective of the route of administration [see Dosage and Administration (2.5) and Use in Specific Populations (8.7)].

Racial or Ethnic Groups

The pharmacokinetics of tacrolimus have been studied following single IV and oral administration of tacrolimus to 10 African-American, 12 Latino-American, and 12 Caucasian healthy volunteers. There were no significant pharmacokinetic differences among the three ethnic groups following a 4-hour IV infusion of 0.015 mg/kg. However, after single oral administration of 5 mg, mean (± SD) tacrolimus Cmax in African-Americans (23.6 ± 12.1 ng/mL) was significantly lower than in Caucasians (40.2 ± 12.6 ng/mL) and the Latino-Americans (36.2 ± 15.8 ng/mL) (p < 0.01). Mean AUC0 to inf tended to be lower in African-Americans (203 ± 115 ng·hr/mL) than Caucasians (344 ± 186 ng·hr/mL) and Latino-Americans (274 ± 150 ng·hr/mL). The mean (± SD) absolute oral bioavailability (F) in African-Americans (12 ± 4.5%) and Latino-Americans (14 ± 7.4%) was significantly lower than in Caucasians (19 ± 5.8%, p = 0.011). There was no significant difference in mean terminal T1/2 among the three ethnic groups (range from approximately 25 to 30 hours). A retrospective comparison of African-American and Caucasian kidney transplant patients indicated that African-American patients required higher tacrolimus doses to attain similar trough concentrations [see Dosage and Administration (2.2)].

Male and Female Patients

A formal trial to evaluate the effect of gender on tacrolimus pharmacokinetics has not been conducted, however, there was no difference in dosing by gender in the kidney transplant trial. A retrospective comparison of pharmacokinetics in healthy volunteers, and in kidney, liver, and heart transplant patients indicated no gender-based differences.

Drug Interaction Studies

Frequent monitoring of whole blood concentrations and appropriate dosage adjustments of tacrolimus are recommended when concomitant use of the following drugs with tacrolimus is initiated or discontinued [see Drug Interactions (7)].

- Telaprevir: In a single-dose study in 9 healthy volunteers, co-administration of tacrolimus (0.5 mg single dose) with telaprevir (750 mg three times daily for 13 days) increased the tacrolimus dose-normalized Cmax by 9.3-fold and AUC by 70-fold compared to tacrolimus alone [see Drug Interactions (7.2)].
- Boceprevir: In a single-dose study in 12 subjects, co-administration of tacrolimus (0.5 mg single dose) with boceprevir (800 mg three times daily for 11 days) increased tacrolimus Cmax by 9.9-fold and AUC by 17-fold compared to tacrolimus alone [see Drug Interactions (7.2)].
- Nelfinavir: Based on a clinical study of 5 liver transplant recipients, co-administration of tacrolimus with nelfinavir increased blood concentrations of tacrolimus significantly and, as a result, a reduction in the tacrolimus dose by an average of 16-fold was needed to maintain mean trough tacrolimus blood concentrations of 9.7 ng/mL. It is recommended to avoid concomitant use of tacrolimus and nelfinavir unless the benefits outweigh the risks [see Drug Interactions (7.2)].
- Rifampin: In a study of 6 normal volunteers, a significant decrease in tacrolimus oral bioavailability (14 ± 6% vs. 7 ± 3%) was observed with concomitant rifampin administration (600 mg). In addition, there was a significant increase in tacrolimus clearance (0.036 ± 0.008 L/hr/kg vs. 0.053 ± 0.010 L/hr/kg) with concomitant rifampin administration [see Drug Interactions (7.2)].
- Magnesium and Aluminum-hydroxide: In a single-dose crossover study in healthy volunteers, co-administration of tacrolimus and magnesium-aluminum-hydroxide resulted in a 21% increase in the mean tacrolimus AUC and a 10% decrease in the mean tacrolimus Cmax relative to tacrolimus administration alone [see Drug Interactions (7.2)].
- Ketoconazole: In a study of 6 normal volunteers, a significant increase in tacrolimus oral bioavailability (14 ± 5% vs. 30 ± 8%) was observed with concomitant ketoconazole administration (200 mg). The apparent oral clearance of tacrolimus during ketoconazole administration was significantly decreased compared to tacrolimus alone (0.430 ± 0.129 L/hr/kg vs. 0.148 ± 0.043 L/hr/kg). Overall, IV clearance of tacrolimus was not significantly changed by ketoconazole co-administration, although it was highly variable between patients [see Drug Interactions (7.2)].
- Voriconazole (see complete prescribing information for VFEND): Repeat oral dose administration of voriconazole (400 mg every 12 hours for one day, then 200 mg every 12 hours for 6 days) increased tacrolimus (0.1 mg/kg single dose) Cmax and AUCτ in healthy subjects by an average of 2-fold (90% CI: 1.9, 2.5) and 3-fold (90% CI: 2.7, 3.8), respectively [see Drug Interactions (7.2)].
- Posaconazole (see complete prescribing information for Noxafil): Repeat oral administration of posaconazole (400 mg twice daily for 7 days) increased tacrolimus (0.05 mg/kg single dose) Cmax and AUC in healthy subjects by an average of 2-fold (90% CI: 2.01, 2.42) and 4.5-fold (90% CI 4.03, 5.19), respectively [see Drug Interactions (7.2)].
- Caspofungin (see complete prescribing information for CANCIDAS): Caspofungin reduced the blood AUC0 to 12 of tacrolimus by approximately 20%, peak blood concentration (Cmax) by 16%, and 12-hour blood concentration (C12hr) by 26% in healthy adult subjects when tacrolimus (2 doses of 0.1 mg/kg 12 hours apart) was administered on the 10th day of CANCIDAS 70 mg daily, as compared to results from a control period in which tacrolimus was administered alone [see Drug Interactions (7.2)]. The mechanism of interaction has not been confirmed.

13 NONCLINICAL TOXICOLOGY

13.1 Carcinogenesis, Mutagenesis, Impairment of Fertility

Carcinogenesis

Carcinogenicity studies were conducted in male and female rats and mice. In the 80-week mouse oral study and in the 104-week rat oral study, no relationship of tumor incidence to tacrolimus dosage was found. The highest dose used in the mouse was 3 mg/kg/day (0.9 to 2.2 times the AUC at clinical doses of 0.075 to 0.2 mg/kg/day) and in the rat was 5 mg/kg/day (0.265 to 0.65 times the AUC at clinical doses of 0.075 to 0.2 mg/kg/day) [see Warnings and Precautions (5.1)].

A 104-week dermal carcinogenicity study was performed in mice with tacrolimus ointment (0.03% to 3%), equivalent to tacrolimus doses of 1.1 to 118 mg/kg/day or 3.3 to 354 mg/m^2/day. In the study, the incidence of skin tumors was minimal and the topical application of tacrolimus was not associated with skin tumor formation under ambient room lighting. However, a statistically significant elevation in the incidence of pleomorphic lymphoma in high-dose male (25/50) and female animals (27/50) and in the incidence of undifferentiated lymphoma in high-dose female animals (13/50) was noted in the mouse dermal carcinogenicity study. Lymphomas were noted in the mouse dermal carcinogenicity study at a daily dose of 3.5 mg/kg (0.1% tacrolimus ointment). No drug-related tumors were noted in the mouse dermal carcinogenicity study at a daily dose of 1.1 mg/kg (0.03% tacrolimus ointment). The relevance of topical administration of tacrolimus in the setting of systemic tacrolimus use is unknown.

The implications of these carcinogenicity studies to the human condition are limited; doses of tacrolimus were administered that likely induced immunosuppression in these animals, impairing their immune system’s ability to inhibit unrelated carcinogenesis.

Mutagenesis

No evidence of genotoxicity was seen in bacterial (Salmonella and E. coli) or mammalian (Chinese hamster lung-derived cells) in vitro assays of mutagenicity, the in vitro CHO/HGPRT assay of mutagenicity, or in vivo clastogenicity assays performed in mice; tacrolimus did not cause unscheduled DNA synthesis in rodent hepatocytes.

Impairment of Fertility

Tacrolimus, subcutaneously administered to male rats at paternally toxic doses of 2 mg/kg/day (1.6 to 4.3 times the recommended clinical dose range [0.2 to 0.075 mg/kg/day] on a mg/m^2 basis) or 3 mg/kg/day (2.4 to 6.4 times the recommended clinical dose range), resulted in a dose-related decrease in sperm count. Tacrolimus, administered orally at 1 mg/kg (0.8 to 2.2 times the clinical dose range) to male and female rats, prior to and during mating, as well as to dams during gestation and lactation, was associated with embryolethality and adverse effects on female reproduction. Effects on female reproductive function (parturition) and embryolethal effects were indicated by a higher rate of pre- and post-implantation loss and increased numbers of undelivered and nonviable pups. When administered at 3.2 mg/kg (2.6 to 6.9 times the clinical dose range based on body surface area), tacrolimus was associated with maternal and paternal toxicity as well as reproductive toxicity including marked adverse effects on estrus cycles, parturition, pup viability, and pup malformations.

14 CLINICAL STUDIES

14.1 Kidney Transplantation

Tacrolimus/Azathioprine (AZA)

Tacrolimus-based immunosuppression in conjunction with azathioprine and corticosteroids following kidney transplantation was assessed in a randomized, multicenter, non-blinded, prospective trial. There were 412 kidney transplant patients enrolled at 19 clinical sites in the United States. Study therapy was initiated when renal function was stable as indicated by a serum creatinine ≤ 4 mg/dL (median of 4 days after transplantation, range 1 to 14 days). Patients less than 6 years of age were excluded.

There were 205 patients randomized to tacrolimus-based immunosuppression and 207 patients were randomized to cyclosporine-based immunosuppression. All patients received prophylactic induction therapy consisting of an antilymphocyte antibody preparation, corticosteroids, and azathioprine. Overall, 1-year patient and graft survivals were 96.1% and 89.6%, respectively.

Data from this trial of tacrolimus in conjunction with azathioprine indicate that during the first 3 months of that trial, 80% of the patients maintained trough concentrations between 7 to 20 ng/mL, and then between 5 to 15 ng/mL, through 1 year.

Tacrolimus/Mycophenolate Mofetil (MMF)

Tacrolimus-based immunosuppression in conjunction with MMF, corticosteroids, and induction has been studied. In a randomized, open-label, multicenter trial (Study 1), 1589 kidney transplant patients received tacrolimus (Group C, n = 401), sirolimus (Group D, n = 399), or one of two cyclosporine (CsA) regimens (Group A, n = 390 and Group B, n = 399) in combination with MMF and corticosteroids; all patients, except those in one of the two cyclosporine groups, also received induction with daclizumab. The trial was conducted outside the United States; the trial population was 93% Caucasian. In this trial, mortality at 12 months in patients receiving tacrolimus/MMF was similar (3%) compared to patients receiving cyclosporine/MMF (3% and 2%) or sirolimus/MMF (3%). Patients in the tacrolimus group exhibited higher estimated creatinine clearance rates (eCLcr) using the Cockcroft-Gault formula (Table 20) and experienced fewer efficacy failures, defined as biopsy-proven acute rejection (BPAR), graft loss, death, and/or loss to follow-up (Table 21) in comparison to each of the other three groups. Patients randomized to tacrolimus/MMF were more likely to develop diarrhea and diabetes after the transplantation and experienced similar rates of infections compared to patients randomized to either cyclosporine/MMF regimen [see Adverse Reactions (6.1)].

Table 20. Estimated Creatinine Clearance at 12 Months (Study 1)

Group | eCLcr [mL/min] at Month 12*
Group | N | MEAN | SD | MEDIAN | Treatment Difference with Group C (99.2% CI†)
(A) CsA/MMF/CS | 390 | 56.5 | 25.8 | 56.9 | -8.6 (-13.7, -3.7)
(B) CsA/MMF/CS/Daclizumab | 399 | 58.9 | 25.6 | 60.9 | -6.2 (-11.2, -1.2)
(C) Tac/MMF/CS/Daclizumab | 401 | 65.1 | 27.4 | 66.2 | -
(D) Siro/MMF/CS/Daclizumab | 399 | 56.2 | 27.4 | 57.3 | -8.9 (-14.1, -3.9)
Total | 1589 | 59.2 | 26.8 | 60.5
Key: CsA = Cyclosporine, CS = Corticosteroids, Tac = Tacrolimus, Siro = Sirolimus

*All death/graft loss (n = 41, 27, 23, and 42 in Groups A, B, C, and D) and patients whose last recorded creatinine values were prior to month 3 visit (n = 10, 9, 7, and 9 in Groups A, B, C, and D, respectively) were imputed with Glomerular Filtration Rate (GFR) of 10 mL/min; a subject's last observed creatinine value from month 3 on was used for the remainder of subjects with missing creatinine at month 12 (n = 11, 12, 15, and 19 for Groups A, B, C, and D, respectively). Weight was also imputed in the calculation of estimated GFR, if missing.

†Adjusted for multiple (6) pairwise comparisons using Bonferroni corrections.

Table 21. Incidence of BPAR, Graft Loss, Death, or Loss to Follow-up at 12 Months (Study 1)

 | Group A; N = 390 | Group B; N = 399 | Group C; N = 401 | Group D; N = 399
Overall Failure | 141 (36.2%) | 126 (31.6%) | 82 (20.4%) | 185 (46.4%)
Components of efficacy failure
BPAR | 113 (29%) | 106 (26.6%) | 60 (15%) | 152 (38.1%)
Graft loss excluding death | 28 (7.2%) | 20 (5%) | 12 (3%) | 30 (7.5%)
Mortality | 13 (3.3%) | 7 (1.8%) | 11 (2.7%) | 12 (3%)
Lost to follow-up | 5 (1.3%) | 7 (1.8%) | 5 (1.3%) | 6 (1.5%)
Treatment Difference of efficacy failure compared to Group C (99.2% CI*) | 15.8%; (7.1%, 24.3%) | 11.2%; (2.7%, 19.5%) | - | 26%; (17.2%, 34.7%)
Key: Group A = CsA/MMF/CS, B = CsA/MMF/CS/Daclizumab, C = Tac/MMF/CS/Daclizumab, and D = Siro/MMF/CS/Daclizumab

*Adjusted for multiple (6) pairwise comparisons using Bonferroni corrections.

The protocol-specified target tacrolimus trough concentrations (Ctrough,Tac) were 3 to 7 ng/mL; however, the observed median Ctroughs,Tac approximated 7 ng/mL throughout the 12-month trial (Table 22). Approximately 80% of patients maintained tacrolimus whole blood concentrations between 4 to 11 ng/mL through 1 year post-transplant.

Table 22. Tacrolimus Whole Blood Trough Concentration Range (Study 1)

Time | Median (P10 to P90*) tacrolimus whole blood trough concentration range (ng/mL)
Day 30 (N = 366) | 6.9 (4.4 to 11.3)
Day 90 (N = 351) | 6.8 (4.1 to 10.7)
Day 180 (N = 355) | 6.5 (4 to 9.6)
Day 365 (N = 346) | 6.5 (3.8 to 10)

*10 to 90th Percentile: range of Ctrough,Tac that excludes lowest 10% and highest 10% of Ctrough,Tac

The protocol-specified target cyclosporine trough concentrations (Ctrough,CsA) for Group B were 50 to 100 ng/mL; however, the observed median Ctroughs,CsA approximated 100 ng/mL throughout the 12-month trial. The protocol-specified target Ctroughs,CsA for Group A were 150 to 300 ng/mL for the first 3 months and 100 to 200 ng/mL from month 4 to month 12; the observed median Ctroughs,CsA approximated 225 ng/mL for the first 3 months and 140 ng/mL from month 4 to month 12.

While patients in all groups started MMF at 1 gram twice daily, the MMF dose was reduced to less than 2 g per day in 63% of patients in the tacrolimus treatment arm by month 12 (Table 23); approximately 50% of these MMF dose reductions were due to adverse reactions. By comparison, the MMF dose was reduced to less than 2 g per day in 49% and 45% of patients in the two cyclosporine arms (Group A and Group B, respectively), by month 12 and approximately 40% of MMF dose reductions were due to adverse reactions.

Table 23. MMF Dose Over Time in Tacrolimus/MMF (Group C) (Study 1)

Time period (Days) | Time-averaged MMF dose (grams per day)*
Time period (Days) | Less than 2 | 2 | Greater than 2
0 to 30 (N = 364) | 37% | 60% | 2%
0 to 90 (N = 373) | 47% | 51% | 2%
0 to 180 (N = 377) | 56% | 42% | 2%
0 to 365 (N = 380) | 63% | 36% | 1%
Key: Time-averaged MMF dose = (total MMF dose)/(duration of treatment)

*Percentage of patients for each time-averaged MMF dose range during various treatment periods. Administration of 2 g per day of time-averaged MMF dose means that MMF dose was not reduced in those patients during the treatment periods.

In a second randomized, open-label, multicenter trial (Study 2), 424 kidney transplant patients received tacrolimus (N = 212) or cyclosporine (N = 212) in combination with MMF 1 gram twice daily, basiliximab induction, and corticosteroids. In this trial, the rate for the combined endpoint of BPAR, graft failure, death, and/or lost to follow-up at 12 months in the tacrolimus/MMF group was similar to the rate in the cyclosporine/MMF group. There was, however, an imbalance in mortality at 12 months in those patients receiving tacrolimus /MMF (4%) compared to those receiving cyclosporine/MMF (2%), including cases attributed to over-immunosuppression (Table 24).

Table 24. Incidence of BPAR, Graft Loss, Death, or Loss to Follow-up at 12 Months (Study 2)

 | Tacrolimus/MMF; (N = 212) | Cyclosporine/MMF; (N = 212)
Overall Failure | 32 (15.1%) | 36 (17%)
Components of efficacy failure
BPAR | 16 (7.5%) | 29 (13.7%)
Graft loss excluding death | 6 (2.8%) | 4 (1.9%)
Mortality | 9 (4.2%) | 5 (2.4%)
Lost to follow-up | 4 (1.9%) | 1 (0.5%)
Treatment Difference of efficacy failure compared to tacrolimus /MMF group (95% CI*) |  | 1.9% (-5.2%, 9%)

*95% confidence interval calculated using Fisher's Exact Test.

The protocol-specified target tacrolimus whole blood trough concentrations (Ctrough,Tac) in Study 2 were 7 to 16 ng/mL for the first three months and 5 to 15 ng/mL thereafter. The observed median Ctroughs,Tac approximated 10 ng/mL during the first three months and 8 ng/mL from month 4 to month 12 (Table 25). Approximately 80% of patients maintained tacrolimus whole blood trough concentrations between 6 to 16 ng/mL during months 1 through 3 and, then, between 5 to 12 ng/mL from month 4 through 1 year.

Table 25. Tacrolimus Whole Blood Trough Concentration Range (Study 2)

Time | Median (P10 to P90*) tacrolimus whole blood trough concentration range
Time | (ng/mL)
Day 30 (N = 174) | 10.5 (6.3 to 16.8)
Day 60 (N = 179) | 9.2 (5.9 to 15.3)
Day 120 (N = 176) | 8.3 (4.6 to 13.3)
Day 180 (N = 171) | 7.8 (5.5 to 13.2)
Day 365 (N = 178) | 7.1 (4.2 to 12.4)

*10 to 90th Percentile: range of Ctrough,Tac that excludes lowest 10% and highest 10% of Ctrough,Tac.

The protocol-specified target cyclosporine whole blood concentrations (Ctrough,CsA) were 125 to 400 ng/mL for the first three months, and 100 to 300 ng/mL thereafter. The observed median Ctroughs,CsA approximated 280 ng/mL during the first three months and 190 ng/mL from month 4 to month 12.

Patients in both groups started MMF at 1 gram twice daily. The MMF dose was reduced to less than 2 grams per day by month 12 in 62% of patients in the tacrolimus capsules /MMF group (Table 26) and in 47% of patients in the cyclosporine/MMF group. Approximately 63% and 55% of these MMF dose reductions were because of adverse reactions in the tacrolimus capsules /MMF group and the cyclosporine/MMF group, respectively [see Adverse Reactions (6.1)].

Table 26. MMF Dose Over Time in the Tacrolimus/MMF Group (Study 2)

Time period (Days) | Time-averaged MMF dose (g/day)*
Time period (Days) | Less than 2 | 2 | Greater than 2
0 to 30 (N = 212) | 25% | 69% | 6%
0 to 90 (N = 212) | 41% | 53% | 6%
0 to 180 (N = 212) | 52% | 41% | 7%
0 to 365 (N = 212) | 62% | 34% | 4%
Key: Time-averaged MMF dose=(total MMF dose)/(duration of treatment)

*Percentage of patients for each time-averaged MMF dose range during various treatment periods. Two grams per day of time- averaged MMF dose means that the MMF dose was not reduced in those patients during the treatment periods.

14.2 Liver Transplantation

The safety and efficacy of tacrolimus-based immunosuppression following orthotopic liver transplantation were assessed in two prospective, randomized, non-blinded multicenter trials. The active control groups were treated with a cyclosporine-based immunosuppressive regimen (CsA/AZA). Both trials used concomitant adrenal corticosteroids as part of the immunosuppressive regimens. These trials compared patient and graft survival rates at 12 months following transplantation.

In one trial, 529 patients were enrolled at 12 clinical sites in the United States; prior to surgery, 263 were randomized to the tacrolimus-based immunosuppressive regimen and 266 to the CsA/AZA. In 10 of the 12 sites, the same CsA/AZA protocol was used, while 2 sites used different control protocols. This trial excluded patients with renal dysfunction, fulminant hepatic failure with Stage IV encephalopathy, and cancers; pediatric patients (≤ 12 years old) were allowed.

In the second trial, 545 patients were enrolled at 8 clinical sites in Europe; prior to surgery, 270 were randomized to the tacrolimus-based immunosuppressive regimen and 275 to CsA/AZA. In this trial, each center used its local standard CsA/AZA protocol in the active-control arm. This trial excluded pediatric patients, but did allow enrollment of subjects with renal dysfunction, fulminant hepatic failure in Stage IV encephalopathy, and cancers other than primary hepatic with metastases.

One-year patient survival and graft survival in the tacrolimus-based treatment groups were similar to those in the CsA/AZA treatment groups in both trials. The overall 1-year patient survival (CsA/AZA and tacrolimus-based treatment groups combined) was 88% in the U.S. trial and 78% in the European trial. The overall 1-year graft survival (CsA/AZA and tacrolimus-based treatment groups combined) was 81% in the U.S. trial and 73% in the European trial. In both trials, the median time to convert from IV to oral tacrolimus dosing was 2 days.

Although there is a lack of direct correlation between tacrolimus concentrations and drug efficacy, data from clinical trials of liver transplant patients have shown an increasing incidence of adverse reactions with increasing trough blood concentrations. Most patients are stable when trough whole blood concentrations are maintained between 5 to 20 ng/mL. Long-term post-transplant patients are often maintained at the low end of this target range.

Data from the U.S. clinical trial show that the median trough blood concentrations, measured at intervals from the second week to one year post-transplantation, ranged from 9.8 to 19.4 ng/mL.

14.3 Heart Transplantation

Two open-label, randomized, comparative trials evaluated the safety and efficacy of tacrolimus-based and cyclosporine-based immunosuppression in primary orthotopic heart transplantation. In a trial conducted in Europe, 314 patients received a regimen of antibody induction, corticosteroids, and azathioprine in combination with tacrolimus or cyclosporine modified for 18 months. In a 3-arm trial conducted in the U.S., 331 patients received corticosteroids and tacrolimus plus sirolimus, tacrolimus plus mycophenolate mofetil (MMF) or cyclosporine modified plus MMF for 1 year.

In the European trial, patient/graft survival at 18 months post-transplant was similar between treatment arms, 92% in the tacrolimus group and 90% in the cyclosporine group. In the U.S. trial, patient and graft survival at 12 months was similar with 93% survival in the tacrolimus plus MMF group and 86% survival in the cyclosporine modified plus MMF group. In the European trial, the cyclosporine trough concentrations were above the pre-defined target range (i.e., 100 to 200 ng/mL) at Day 122 and beyond in 32% to 68% of the patients in the cyclosporine treatment arm, whereas the tacrolimus trough concentrations were within the pre-defined target range (i.e., 5 to 15 ng/mL) in 74% to 86% of the patients in the tacrolimus treatment arm. Data from this European trial indicate that from 1 week to 3 months post-transplant, approximately 80% of patients maintained trough concentrations between 8 to 20 ng/mL and, from 3 months through 18 months post-transplant, approximately 80% of patients maintained trough concentrations between 6 to 18 ng/mL.

The U.S. trial contained a third arm of a combination regimen of sirolimus, 2 mg per day, and full-dose tacrolimus; however, this regimen was associated with increased risk of wound-healing complications, renal function impairment, and insulin-dependent post-transplant diabetes mellitus, and is not recommended [see Warnings and Precautions (5.10)].

15 REFERENCES

1. “OSHA Hazardous Drugs.” OSHA. http://www.osha.gov/SLTC/hazardousdrugs/index.html

16 HOW SUPPLIED/STORAGE AND HANDLING

16.1 Tacrolimus Capsules, USP

Tacrolimus Capsules, USP are available as follows:

0.5 mg: Size “4” hard gelatin capsule with light yellow cap and light yellow body, imprinted with a Glenmark logo “G” on the cap and “685” on the body in red ink, filled with white to off-white granular powder.

Bottles of 100 with child-resistant closure, NDC 68462-685-01

1 mg: Size “4” hard gelatin capsule with white cap and white body, imprinted with a Glenmark logo “G” on the cap and “686” on the body in red ink, filled with white to off-white granular powder.

Bottles of 100 with child-resistant closure, NDC 68462-686-01

Cartons of 100 (10 x 10 unit-dose), NDC 68462-686-14

5 mg: Size “4” hard gelatin capsule with greyish red cap and greyish red body, imprinted with a Glenmark logo “G” on the cap and “687” on the body in white ink, filled with white to off-white granular powder.

Bottles of 100 with child-resistant closure, NDC 68462-687-01

Cartons of 100 (10 x 10 unit-dose), NDC 68462-687-14

Note: Tacrolimus Capsules, USP are not filled to maximum capsule capacity. Capsule contains labeled amount.

Store and Dispense

Store at 20°C to 25°C (68°F to 77°F); excursions permitted to 15°C to 30°C (59°F to 86°F) [see USP Controlled Room Temperature].

16.4 Handling and Disposal

Tacrolimus can cause fetal harm. Tacrolimus capsules should not be opened or crushed. Wearing disposable gloves is recommended during dilution of the injection in the hospital and when wiping any spills. Avoid inhalation or direct contact with skin or mucous membranes of the powder contained in tacrolimus capsules. If such contact occurs, wash the skin thoroughly with soap and water; if ocular contact occurs, rinse eyes with water. In case a spill occurs, wipe the surface with a wet paper towel. Follow applicable special handling and disposal procedures^1.

17 PATIENT COUNSELING INFORMATION

Advise the patient to read the FDA-approved patient labeling (Patient Information and Instructions for Use).

17.1 Administration

Advise the patient or caregiver to:

- Inspect their tacrolimus capsules medicine when they receive a new prescription and before taking it. If the appearance of the capsule is not the same as usual, or if dosage instructions have changed, advise patients to contact their healthcare provider as soon as possible to make sure that they have the right medicine. Other tacrolimus products cannot be substituted for tacrolimus capsules.
- Take tacrolimus capsules at the same 12-hour intervals every day to achieve consistent blood concentrations.
- Take tacrolimus capsules consistently either with or without food because the presence and composition of food decreases the bioavailability of tacrolimus capsules.
- Not to eat grapefruit or drink grapefruit juice in combination with tacrolimus capsules [see Drug Interactions (7.2)].

17.2 Development of Lymphoma and Other Malignancies

Inform patients they are at increased risk of developing lymphomas and other malignancies, particularly of the skin, due to immunosuppression. Advise patients to limit exposure to sunlight and ultraviolet (UV) light by wearing protective clothing and using a broad spectrum sunscreen with a high protection factor [see Warnings and Precautions (5.1)].

17.3 Increased Risk of Infection

Inform patients they are at increased risk of developing a variety of infections, including opportunistic infections, due to immunosuppression and to contact their physician if they develop any symptoms of infection such as fever, sweats or chills, cough or flu-like symptoms, muscle aches, or warm, red, painful areas on the skin [see Warnings and Precautions (5.2)].

17.4 New Onset Diabetes After Transplant

Inform patients that tacrolimus capsules can cause diabetes mellitus and should be advised to contact their physician if they develop frequent urination, increased thirst, or hunger [see Warnings and Precautions (5.4)].

17.5 Nephrotoxicity

Inform patients that tacrolimus can have toxic effects on the kidney that should be monitored. Advise patients to attend all visits and complete all blood tests ordered by their medical team [see Warnings and Precautions (5.5)].

17.6 Neurotoxicity

Inform patients that they are at risk of developing adverse neurologic reactions including seizure, altered mental status, and tremor. Advise patients to contact their physician should they develop vision changes, delirium, or tremors [see Warnings and Precautions (5.6)].

17.7 Hyperkalemia

Inform patients that tacrolimus can cause hyperkalemia. Monitoring of potassium levels may be necessary, especially with concomitant use of other drugs known to cause hyperkalemia [see Warnings and Precautions (5.7)].

17.8 Hypertension

Inform patients that tacrolimus capsules can cause high blood pressure which may require treatment with antihypertensive therapy. Advise patients to monitor their blood pressure [see Warnings and Precautions (5.8)].

17.9 Thrombotic Microangiopathy

Inform patients that tacrolimus capsules can cause blood clotting problems. The risk of this occurring increases when patients take tacrolimus and sirolimus or everolimus concomitantly, or when patients develop certain infections. Advise them to seek medical attention promptly if they develop fever, petequiae or bruises, fatigue, confusion, jaundice, oliguria. [see Warnings and Precautions (5.16)].

17.10 Drug Interactions

Instruct patients to tell their healthcare providers when they start or stop taking any medicines, including prescription medicines and nonprescription medicines, natural or herbal remedies, nutritional supplements, and vitamins. Advise patients to avoid grapefruit and grapefruit juice [see Drug Interactions (7)].

17.11 Pregnancy, Lactation and Infertility

Inform women of childbearing potential that tacrolimus capsules can harm the fetus. Instruct male and female patients to discuss with their healthcare provider family planning options including appropriate contraception. Also, discuss with pregnant patients the risks and benefits of breastfeeding their infant [see Use in Specific Populations (8.1, 8.2, 8.3)].

Encourage female transplant patients who become pregnant and male patients who have fathered a pregnancy, exposed to immunosuppressants including tacrolimus, to enroll in the voluntary Transplantation Pregnancy Registry International. To enroll or register, patients can call the toll free number 1-877-955-6877 or https://www.transplantpregnancyregistry.org/[see Use in Specific Populations (8.1)].

Based on animal studies, tacrolimus capsules may affect fertility in males and females [see Nonclinical Toxicology (13.1)].

17.12 Myocardial Hypertrophy

Inform patients to report symptoms of tiredness, swelling, and/or shortness of breath (heart failure).

17.13 Immunizations

Inform patients that tacrolimus capsules can interfere with the usual response to immunizations and that they should avoid live vaccines [see Warnings and Precautions (5.14)].

*Brands listed are the trademarks of their respective owners.

Distributed by:

Glenmark Pharmaceuticals Inc., USA

Elmwood Park, NJ 07407

Questions? 1 (888) 721-7115

www.glenmarkpharma-us.com

October 2025

Patient Information

Tacrolimus

(ta-KROE-li-mus)

Capsules

Read this Patient Information before you start taking tacrolimus capsules and each time you get a refill. There may be new information. This information does not take the place of talking with your healthcare provider about your medical condition or your treatment.

What is the most important information I should know about tacrolimus capsules?

Tacrolimus capsules can cause serious side effects, including:

- Increased risk of cancer. People who take tacrolimus capsules have an increased risk of getting some kinds of cancer, including skin and lymph gland cancer (lymphoma).
- Increased risk of infection. Tacrolimus capsules is a medicine that affects your immune system. Tacrolimus capsules can lower the ability of your immune system to fight infections. Serious infections can happen in people receiving tacrolimus capsules that can cause death. Call your healthcare provider right away if you have any symptoms of an infection, including:

- fever

- muscle aches

- sweats or chills

- warm, red, or painful areas on your skin

- cough or flu-like symptoms

What are Tacrolimus Capsules?

Tacrolimus capsules are a prescription medicine used with other medicines to help prevent organ rejection in people who have had a kidney, liver, or heart transplant.

Tacrolimus capsules is a type of tacrolimus immediate-release drug and it is not the same as tacrolimus extended-release tablets or tacrolimus extended-release capsules. Your healthcare provider should decide what medicine is right for you.

Who should not take tacrolimus capsules?

Do not take tacrolimus capsules if you are allergic to tacrolimus or any of the ingredients in tacrolimus capsules. See the end of this leaflet for a complete list of ingredients in tacrolimus capsules.

What should I tell my healthcare provider before taking tacrolimus capsules?

Before taking tacrolimus capsules, tell your healthcare provider about all of your medical conditions, including if you:

- plan to receive any vaccines. People taking tacrolimus capsules should not receive live vaccines.
- have or have had liver, kidney, or heart problems.
- are pregnant or plan to become pregnant. Tacrolimus capsules can harm your unborn baby.
  - If you are able to become pregnant, you should use effective birth control before and during treatment with tacrolimus capsules. Talk to your healthcare provider before starting treatment with tacrolimus capsules about birth control methods that may be right for you.
  - Males who have female partners who are able to become pregnant should also use effective birth control before and during treatment with tacrolimus capsules. Talk to your healthcare provider before starting treatment with tacrolimus capsules about birth control methods that may be right for you.
  - There is a pregnancy registry for females who become pregnant and males who have fathered a pregnancy during treatment with tacrolimus capsules. The purpose of this registry is to collect information about the health of you and your baby. To enroll in this voluntary registry, call 1-877-955-6877 or go to https://www.transplantpregnancyregistry.org/.
- are breastfeeding or plan to breastfeed. Tacrolimus passes into your breast milk. You and your healthcare provider should decide if you will breastfeed while taking tacrolimus capsules.
- plan to have children. Tacrolimus capsules may affect the ability to have children in females and males (fertility problems).

Tell your healthcare provider about all the medicines you take, and when you start a new medicine or stop taking a medicine, including prescription and over-the-counter medicines, vitamins, natural, herbal, or nutritional supplements.

Especially tell your healthcare provider if you take:

- sirolimus (RAPAMUNE): You should not take tacrolimus capsules if you take sirolimus
- cyclosporine (GENGRAF, NEORAL, and SANDIMMUNE)
- medicines called aminoglycosides that are used to treat bacterial infections
- ganciclovir (CYTOVENE IV, VALCYTE)
- amphotericin B (ABELCET, AMBISOME)
- cisplatin
- antiviral medicines called nucleoside reverse transcriptase inhibitors
- antiviral medicines called protease inhibitors
- water pill (diuretic)
- medicine to treat high blood pressure
- nelfinavir (VIRACEPT)
- telaprevir (INCIVEK)
- boceprevir
- ritonavir (KALETRA, NORVIR, TECHNIVIE, VIEKIRA PAK, VIEKIRA XR)
- letermovir (PREVYMIS)
- ketoconazole
- itraconazole (ONMEL, SPORANOX)
- voriconazole (VFEND)
- caspofungin (CANCIDAS)
- clarithromycin (BIAXIN, BIAXIN XL, PREVPAC)
- rifampin (RIFADIN, RIFAMATE, RIFATER, RIMACTANE)
- rifabutin (MYCOBUTIN)
- amiodarone (NEXTERONE, PACERONE)
- cannabidiol (EPIDIOLEX)

Ask your healthcare provider or pharmacist if you are not sure if you take any of the medicines listed above. Tacrolimus capsules may affect the way other medicines work, and other medicines may affect how tacrolimus capsules works. Know the medicines you take. Keep a list of your medicines and show it to your healthcare provider and pharmacist when you get a new medicine.

How should I take tacrolimus capsules?

- Take tacrolimus capsules exactly as your healthcare provider tells you to take it.
- Your healthcare provider will tell you how much tacrolimus capsules to take and when to take it.
Your healthcare provider may change your tacrolimus capsules dose if needed. Do not stop taking or change your dose of tacrolimus capsules without talking to your healthcare provider.
- Take tacrolimus capsules with or without food.
- Take tacrolimus capsules the same way every day. For example, if you choose to take tacrolimus capsules with food, you should always take tacrolimus capsules with food.
- Take tacrolimus capsules at the same time each day, 12 hours apart. For example, if you take your first dose at 7:00 a.m., you should take your second dose at 7:00 p.m.
- Taking tacrolimus capsules at the same time each day helps to keep the amount of medicine in your body at a steady level.
- If you take too much tacrolimus capsules, call your healthcare provider or go to the nearest hospital emergency room right away.

Tacrolimus capsules:

- Do not open or crush tacrolimus capsules.

What should I avoid while taking tacrolimus capsules?

- While you take tacrolimus capsules you should not receive any live vaccines.
- Limit the amount of time you spend in sunlight and avoid exposure to ultraviolet (UV) light, such as tanning machines. Wear protective clothing and use a sunscreen with a high sun protection factor (SPF).
- Do not eat grapefruit or drink grapefruit juice during treatment with tacrolimus capsules.

What are the possible side effects of tacrolimus capsules?

Tacrolimus capsules may cause serious side effects, including:

- See “What is the most important information I should know about tacrolimus capsules?”
- problems from medicine errors. People who take tacrolimus capsules have sometimes been given the wrong type of tacrolimus product. Tacrolimus extended-release medicines are not the same as tacrolimus capsules and cannot be substituted for each other. Check your tacrolimus capsules when you get a new prescription and before you take it to make sure you have received tacrolimus capsules.
- Check with the pharmacist and call your healthcare provider if you think you were given the wrong medicine.
- high blood sugar (diabetes). Your healthcare provider may do blood tests to check for diabetes while you take tacrolimus capsules. Call your healthcare provider right away if you have any symptoms of high blood sugar, including:

- frequent urination

- drowsiness

- increased thirst or hunger

- loss of appetite

- blurred vision

- fruity smell on your breath

- confusion

- nausea, vomiting, or stomach pain

- kidney problems. Kidney problems are a serious and common side effect of tacrolimus capsules. Your healthcare provider may do blood tests to check your kidney function while you take tacrolimus capsules.
- nervous system problems. Nervous system problems are a serious and common side effect of tacrolimus capsules. Call your healthcare provider right away if you get any of these symptoms while taking tacrolimus capsules. These could be signs of a serious nervous system problem:

- headache

- changes in behavior

- confusion

- coma

- seizures

- tremors

- changes in your vision

- numbness and tingling

- high levels of potassium in your blood. Your healthcare provider may do blood tests to check your potassium level while you take tacrolimus capsules.
- high blood pressure. High blood pressure is a serious and common side effect of tacrolimus capsules. Your healthcare provider will monitor your blood pressure while you take tacrolimus capsules and may prescribe blood pressure medicine for you, if needed. Your healthcare provider may instruct you to check your blood pressure at home.
- changes in the electrical activity of your heart (QT prolongation).
- heart problems (myocardial hypertrophy). Tell your healthcare provider right away if you get any of these symptoms of heart problems while taking tacrolimus capsules:

- shortness of breath

- feel lightheaded

- chest pain

- feel faint

- severe low red blood cell count (anemia).
- blood clotting problems: Tell your healthcare provider right away if you have fever and bruising under the skin that may appear as red dots, with or without unexplained tiredness, confusion, yellowing of the skin or eyes, decreased urination. When taken with sirolimus or everolimus, the risk of developing these symptoms may increase.

The most common side effects of tacrolimus capsules in people who have received a kidney, liver or heart transplant are:

- infections in general, including cytomegalovirus (cmv) infection

- swelling of the hands, legs, ankles, or feet

- weakness

- tremors (shaking of the body)

- pain

- constipation

- high levels of fat in your blood

- diarrhea

- high levels of potassium in your blood

- headache

- low red blood cell count (anemia)

- stomach pain

- low white blood cell count

- trouble sleeping

- fever

- nausea

- numbness or tingling in your hands and feet

- high blood sugar (diabetes)

- inflammation of your airway (bronchitis)

- low levels of magnesium in your blood

- fluid around your heart

- low levels of phosphate in your blood

Tell your healthcare provider if you have any side effect that bothers you or that does not go away.

These are not all the possible side effects of tacrolimus capsules. For more information, ask your healthcare provider or pharmacist.

Call your doctor for medical advice about side effects. You may report side effects to FDA at 1-800-FDA‑1088.

How should I store Tacrolimus Capsules?

Tacrolimus capsules

Store tacrolimus capsules at room temperature between 20°C to 25°C (68°F to 77°F).

Keep tacrolimus capsules and all medicines out of the reach of children.

General information about the safe and effective use of tacrolimus capsules.

- Medicines are sometimes prescribed for purposes other than those listed in a Patient Information leaflet. Do not use tacrolimus capsules for a condition for which it was not prescribed. Do not give tacrolimus capsules to other people, even if they have the same symptoms that you have. It may harm them. You can ask your pharmacist or healthcare provider for information about tacrolimus capsules that is written for health professionals.
- This Patient Information leaflet summarizes the most important information about tacrolimus capsules. If you would like more information, talk to your healthcare provider.

What are the ingredients in tacrolimus capsules?

Active ingredient: tacrolimus

Inactive ingredients:

croscarmellose sodium, hypromellose, lactose monohydrate and magnesium stearate. The 0.5 mg capsule shell contains D&C Yellow 10, FD&C Red 40, FD&C Blue 1, gelatin, shellac, sodium hydroxide, povidone and titanium dioxide. The 1 mg capsule shell contains FD&C Red 40, gelatin, shellac, sodium hydroxide, povidone and titanium dioxide. The 5 mg capsule shell contains gelatin, D&C Yellow 10, FD&C Blue 1, FD&C Red 40, potassium hydroxide, shellac and titanium dioxide.

*Brands listed are the trademarks of their respective owners.

Distributed by:

Glenmark Pharmaceuticals Inc., USA

Elmwood Park, NJ 07407

Questions? 1 (888) 721-7115

www.glenmarkpharma-us.com

This Patient Information has been approved by the U.S. Food and Drug Administration.

Revised: October 2025